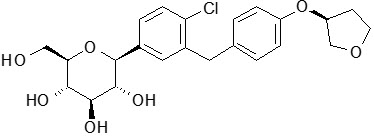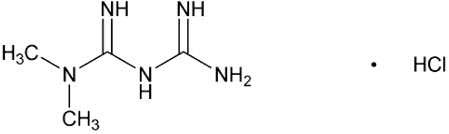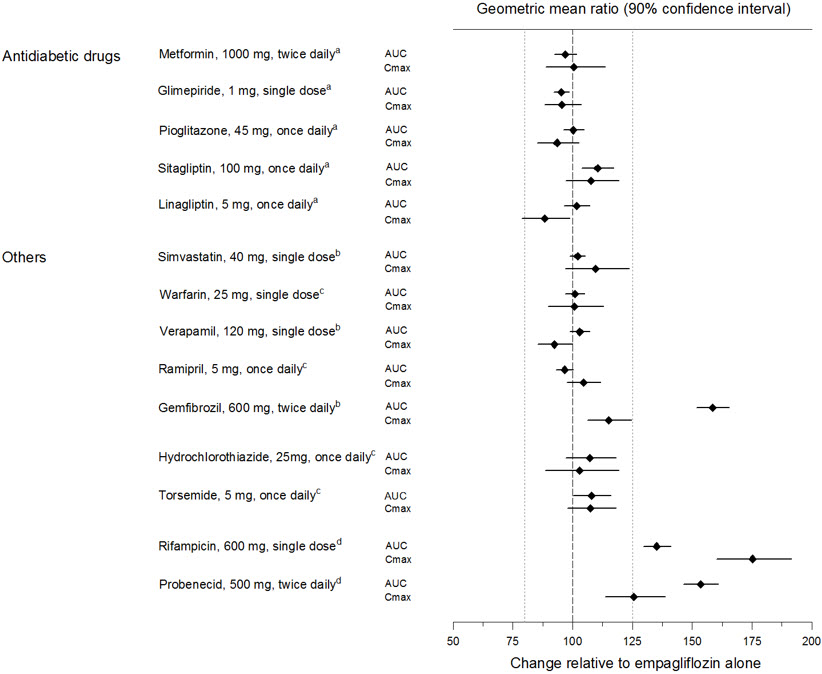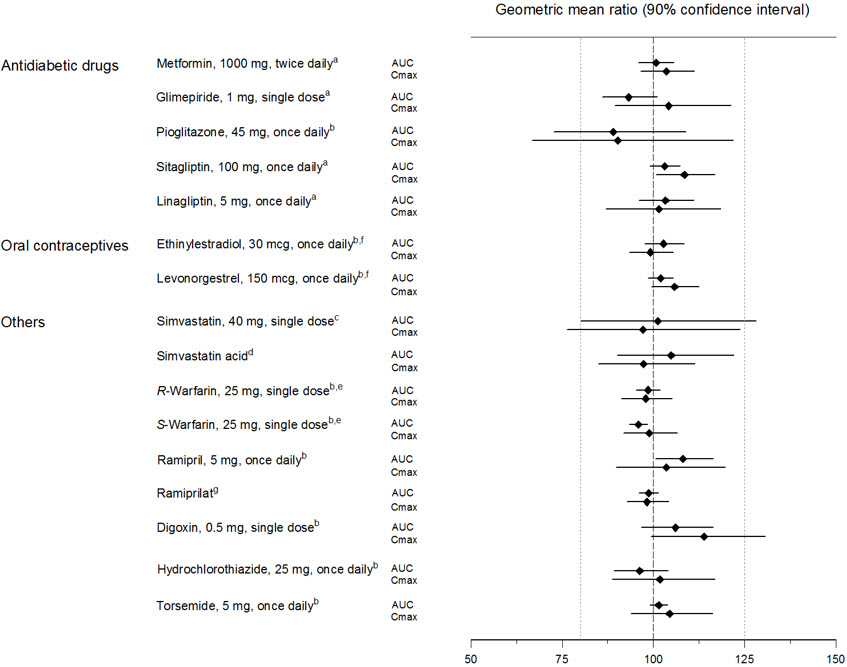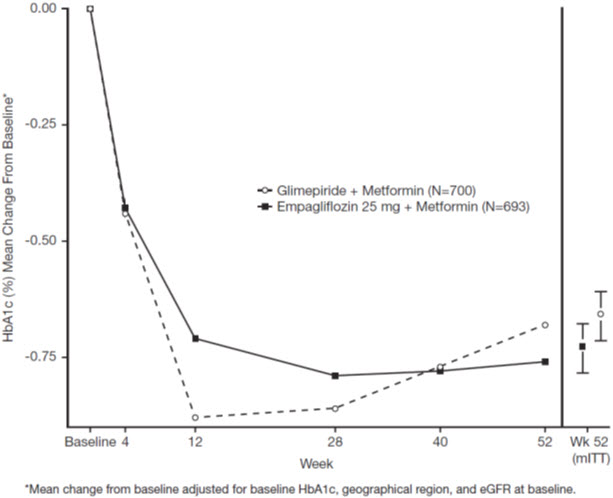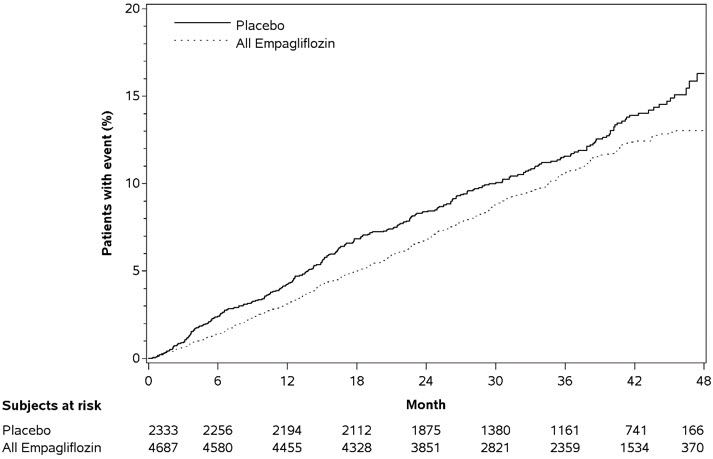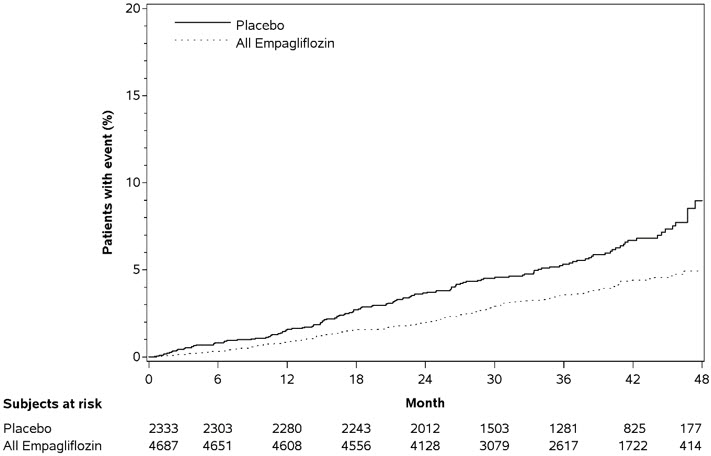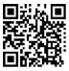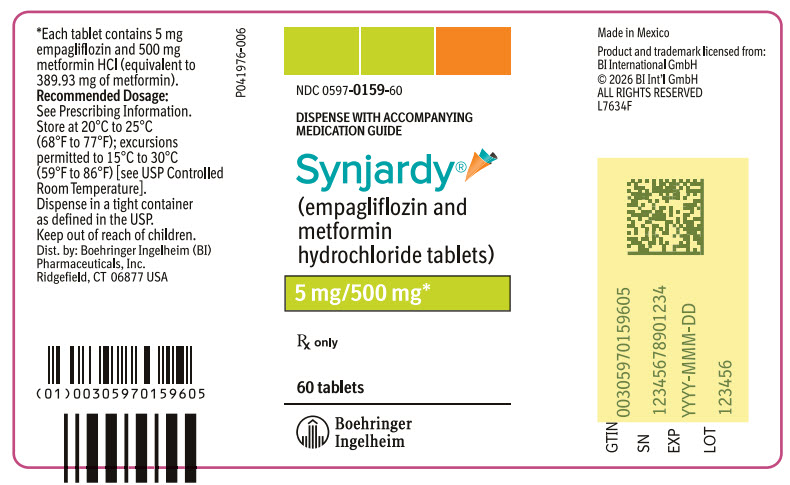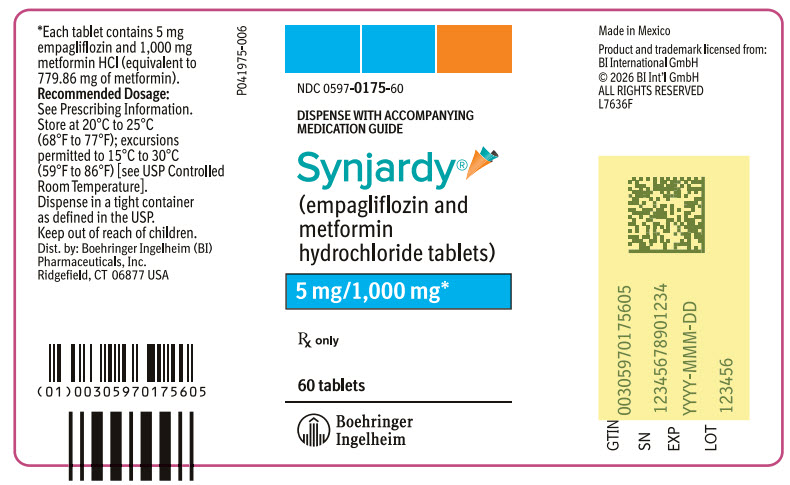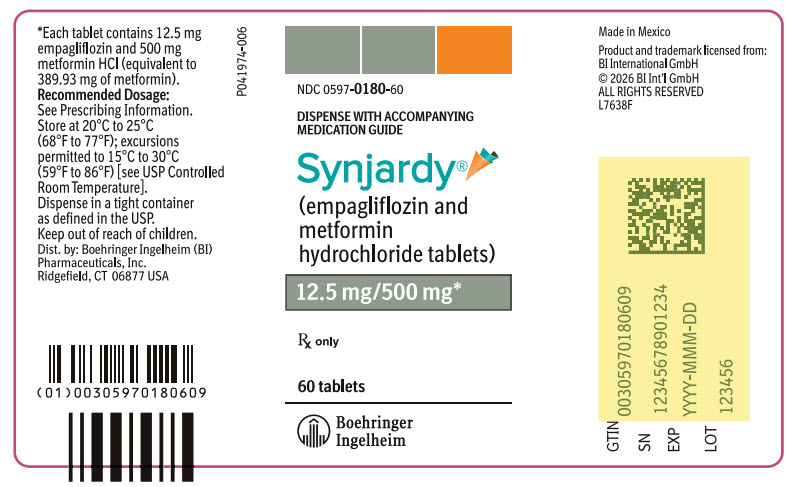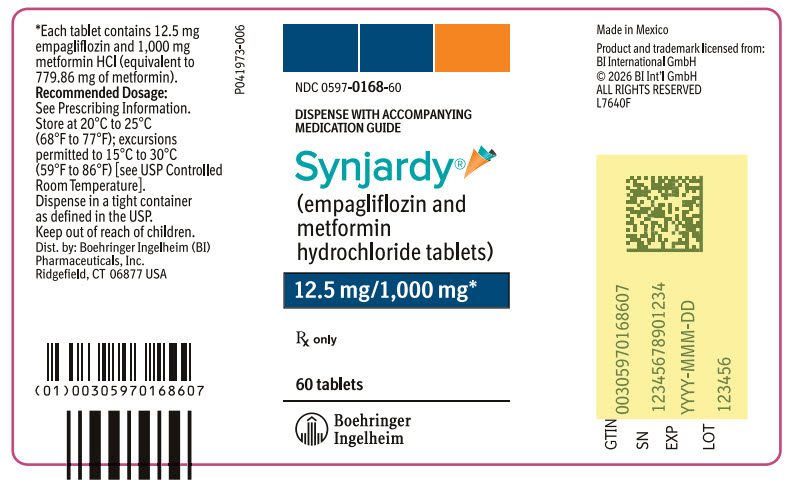 DRUG LABEL: Synjardy
NDC: 0597-0159 | Form: TABLET
Manufacturer: Boehringer Ingelheim Pharmaceuticals, Inc.
Category: prescription | Type: HUMAN PRESCRIPTION DRUG LABEL
Date: 20260130

ACTIVE INGREDIENTS: EMPAGLIFLOZIN 5 mg/1 1; METFORMIN HYDROCHLORIDE 500 mg/1 1

HIGHLIGHTS OF PRESCRIBING INFORMATION

These highlights do not include all the information needed to use SYNJARDY and SYNJARDY XR safely and effectively. See full prescribing information for SYNJARDY and SYNJARDY XR.
SYNJARDY® (empagliflozin and metformin hydrochloride tablets), for oral use
SYNJARDY® XR (empagliflozin and metformin hydrochloride extended-release tablets), for oral use
Initial U.S. Approval: 2015

WARNING: LACTIC ACIDOSIS

See full prescribing information for complete boxed warning.

- Postmarketing cases of metformin-associated lactic acidosis have resulted in death, hypothermia, hypotension, and resistant bradyarrhythmias. Symptoms included malaise, myalgias, respiratory distress, somnolence, and abdominal pain. Laboratory abnormalities included elevated blood lactate levels, anion gap acidosis, increased lactate/pyruvate ratio; and metformin plasma levels generally >5 mcg/mL. (5.1)
- Risk factors include renal impairment, concomitant use of certain drugs, age ≥65 years old, radiological studies with contrast, surgery and other procedures, hypoxic states, excessive alcohol intake, and hepatic impairment. Steps to reduce the risk of and manage metformin-associated lactic acidosis in these high risk groups are provided in the Full Prescribing Information. (5.1)
- If lactic acidosis is suspected, discontinue SYNJARDY or SYNJARDY XR and institute general supportive measures in a hospital setting. Prompt hemodialysis is recommended. (5.1)

RECENT MAJOR CHANGES

Indications and Usage (1) | 3/2025
Warnings and Precautions, Genitourinary Infections, including Urosepsis, Pyelonephritis, Necrotizing Fasciitis of the Perineum (Fournier's Gangrene), and Genital Mycotic Infections (5.4) | 10/2025
Warnings and Precautions, Lower Limb Amputation (5.6) | 3/2025

1 INDICATIONS AND USAGE

SYNJARDY

SYNJARDY is a combination of empagliflozin, a sodium-glucose co-transporter 2 (SGLT2) inhibitor and metformin hydrochloride (HCl) immediate-release, a biguanide, indicated as an adjunct to diet and exercise to improve glycemic control in adults and pediatric patients aged 10 years and older with type 2 diabetes mellitus.

SYNJARDY XR

SYNJARDY XR is a combination of empagliflozin, a SGLT2 inhibitor and metformin HCl extended-release, a biguanide, indicated as an adjunct to diet and exercise to improve glycemic control in adults with type 2 diabetes mellitus.

Empagliflozin

Empagliflozin, when used as a component of SYNJARDY or SYNJARDY XR, is indicated in adults with type 2 diabetes mellitus to reduce the risk of:

- Cardiovascular (CV) death in adults with established CV disease. (1)
- CV death and hospitalization for heart failure in adults with heart failure. (1)
- Sustained decline in eGFR, end-stage kidney disease, CV death, and hospitalization in adults with chronic kidney disease at risk of progression. (1)

Limitations of Use:

- Not recommended for use to improve glycemic control in patients with type 1 diabetes mellitus. It may increase the risk of diabetic ketoacidosis in these patients. (1)
- Because of the metformin HCl component, the use of SYNJARDY or SYNJARDY XR is limited to patients with type 2 diabetes mellitus for all indications. (1)
- Empagliflozin, when used as a component of SYNJARDY or SYNJARDY XR, is not recommended for the treatment of chronic kidney disease in patients with polycystic kidney disease or patients requiring or with a recent history of intravenous immunosuppressive therapy or greater than 45 mg of prednisone or equivalent for kidney disease. Empagliflozin is not expected to be effective in these populations. (1)

2 DOSAGE AND ADMINISTRATION

- Assess renal function before initiating and as clinically indicated. Assess volume status and correct volume depletion before initiating. (2.1)
- Individualize the starting dosage based on the patient's current regimen and renal function. (2.2, 2.3, 2.4)
- The maximum recommended dosage is 25 mg/day of empagliflozin and 2,000 mg/day of metformin HCl. (2.2, 2.3)
- Initiation of SYNJARDY or SYNJARDY XR is not recommended in patients with an eGFR less than 45 mL/min/1.73 m^2, due to the metformin HCl component. (2.4)
- SYNJARDY: take orally twice daily with meals, with gradual dosage escalation to reduce the gastrointestinal adverse reactions due to metformin HCl. (2.2, 2.3)
- SYNJARDY XR: take orally once daily with a meal in the morning, with gradual dosage escalation to reduce the gastrointestinal adverse reactions due to metformin HCl. Swallow whole; do not split, crush, dissolve, or chew. (2.2)
- SYNJARDY or SYNJARDY XR may need to be discontinued at time of, or prior to, iodinated contrast imaging procedures. (2.5)
- Withhold SYNJARDY or SYNJARDY XR at least 3 days, if possible, prior to surgery or procedures associated with prolonged fasting. (2.6)

3 DOSAGE FORMS AND STRENGTHS

SYNJARDY Tablets:

- 5 mg empagliflozin/500 mg metformin HCl (3)
- 5 mg empagliflozin/1,000 mg metformin HCl (3)
- 12.5 mg empagliflozin/500 mg metformin HCl (3)
- 12.5 mg empagliflozin/1,000 mg metformin HCl (3)

SYNJARDY XR Tablets:

- 5 mg empagliflozin/1,000 mg metformin HCl extended-release (3)
- 10 mg empagliflozin/1,000 mg metformin HCl extended-release (3)
- 12.5 mg empagliflozin/1,000 mg metformin HCl extended-release (3)
- 25 mg empagliflozin/1,000 mg metformin HCl extended-release (3)

4 CONTRAINDICATIONS

- Severe renal impairment (eGFR below 30 mL/min/1.73 m^2) (4)
- Metabolic acidosis, including diabetic ketoacidosis (4)
- Hypersensitivity to empagliflozin, metformin HCl or any of the excipients in SYNJARDY or SYNJARDY XR (4)

5 WARNINGS AND PRECAUTIONS

- Diabetic Ketoacidosis in Patients with Type 1 Diabetes Mellitus and Other Ketoacidosis: Consider ketone monitoring in patients at risk of ketoacidosis, as indicated. Assess for ketoacidosis regardless of presenting blood glucose levels and discontinue SYNJARDY or SYNJARDY XR if ketoacidosis is suspected. Monitor patients for resolution of ketoacidosis before restarting. (5.2)
- Volume Depletion: Before initiating SYNJARDY or SYNJARDY XR, assess volume status and renal function in patients with impaired renal function, elderly patients, or patients on loop diuretics. Monitor for signs and symptoms during therapy. (5.3)
- Genitourinary Infections, including Urosepsis, Pyelonephritis, Necrotizing Fasciitis of the Perineum (Fournier's Gangrene), and Genital Mycotic Infections: Monitor patients for signs and symptoms of genitourinary infections and treat promptly, if indicated. Immediately evaluate patients presenting with pain or tenderness, erythema, or swelling in the genital or perineal area, along with fever or malaise, for necrotizing fasciitis and if suspected, discontinue SYNJARDY or SYNJARDY XR, and promptly institute appropriate medical and/or surgical intervention. (5.4)
- Hypoglycemia: Adult patients taking an insulin secretagogue or insulin may have an increased risk of hypoglycemia. In pediatric patients 10 years of age and older, the risk of hypoglycemia was higher regardless of insulin use. Consider lowering the dosage of insulin secretagogue or insulin to reduce the risk of hypoglycemia when initiating SYNJARDY or SYNJARDY XR. (5.5)
- Lower Limb Amputation: Monitor patients for infections or ulcers of lower limbs, and institute appropriate treatment. (5.6)
- Hypersensitivity Reactions: Serious hypersensitivity reactions (e.g., angioedema) have occurred with empagliflozin. If hypersensitivity reactions occur, discontinue SYNJARDY or SYNJARDY XR, treat promptly, and monitor until signs and symptoms resolve. (5.7)
- Vitamin B12 Deficiency: Metformin may lower vitamin B12 levels. Measure hematologic parameters annually and vitamin B12 at 2 to 3 year intervals and manage any abnormalities. (5.8)

6 ADVERSE REACTIONS

- Most common adverse reactions associated with empagliflozin (5% or greater incidence) were urinary tract infections and female genital mycotic infections. (6.1)
- Most common adverse reactions associated with metformin HCl (>5%) are diarrhea, nausea/vomiting, flatulence, abdominal discomfort, indigestion, asthenia, and headache. (6.1)

To report SUSPECTED ADVERSE REACTIONS, contact Boehringer Ingelheim Pharmaceuticals, Inc. at 1-800-542-6257 or FDA at 1-800-FDA-1088 or www.fda.gov/medwatch.

7 DRUG INTERACTIONS

- Carbonic Anhydrase Inhibitors: May increase risk of lactic acidosis. Consider more frequent monitoring. (7)
- Drugs that Reduce Metformin Clearance: May increase risk of lactic acidosis. Consider benefits and risks of concomitant use. (7)
- See full prescribing information for additional drug interactions and information on interference of SYNJARDY or SYNJARDY XR with laboratory tests. (7)

8 USE IN SPECIFIC POPULATIONS

- Pregnancy: Advise females of the potential risk to a fetus especially during the second and third trimesters. (8.1)
- Lactation: Not recommended when breastfeeding. (8.2)
- Females and Males of Reproductive Potential: Advise premenopausal females of the potential for an unintended pregnancy. (8.3)
- Geriatric Patients: Higher incidence of adverse reactions related to volume depletion and reduced renal function. (8.5)
- Renal Impairment: Higher incidence of adverse reactions related to reduced renal function. (8.6)
- Hepatic Impairment: Avoid use in patients with hepatic impairment. (8.7)

FULL PRESCRIBING INFORMATION

WARNING: LACTIC ACIDOSIS

Postmarketing cases of metformin-associated lactic acidosis have resulted in death, hypothermia, hypotension, and resistant bradyarrhythmias. The onset of metformin-associated lactic acidosis is often subtle, accompanied only by nonspecific symptoms such as malaise, myalgias, respiratory distress, somnolence, and abdominal pain. Metformin-associated lactic acidosis was characterized by elevated blood lactate levels (>5 mmol/Liter), anion gap acidosis (without evidence of ketonuria or ketonemia), an increased lactate/pyruvate ratio; and metformin plasma levels generally >5 mcg/mL [see Warnings and Precautions (5.1)].

Risk factors for metformin-associated lactic acidosis include renal impairment, concomitant use of certain drugs (e.g., carbonic anhydrase inhibitors such as topiramate), age 65 years old or greater, having a radiological study with contrast, surgery and other procedures, hypoxic states (e.g., acute congestive heart failure), excessive alcohol intake, and hepatic impairment.

Steps to reduce the risk of and manage metformin-associated lactic acidosis in these high risk groups are provided in the full prescribing information [see Dosage and Administration (2.1), Contraindications (4), Warnings and Precautions (5.1), Drug Interactions (7), and Use in Specific Populations (8.6, 8.7)].

If metformin-associated lactic acidosis is suspected, immediately discontinue SYNJARDY or SYNJARDY XR and institute general supportive measures in a hospital setting. Prompt hemodialysis is recommended [see Warnings and Precautions (5.1)].

1 INDICATIONS AND USAGE

SYNJARDY

SYNJARDY is a combination of empagliflozin and metformin hydrochloride (HCl) immediate-release indicated as an adjunct to diet and exercise to improve glycemic control in adults and pediatric patients aged 10 years and older with type 2 diabetes mellitus.

SYNJARDY XR

SYNJARDY XR is a combination of empagliflozin and metformin HCl extended-release indicated as an adjunct to diet and exercise to improve glycemic control in adults with type 2 diabetes mellitus.

Empagliflozin

Empagliflozin, when used as a component of SYNJARDY or SYNJARDY XR, is indicated in adults with type 2 diabetes mellitus to reduce the risk of:

- Cardiovascular (CV) death in adults with established CV disease.
- CV death and hospitalization for heart failure in adults with heart failure.
- Sustained decline in eGFR, end-stage kidney disease, CV death, and hospitalization in adults with chronic kidney disease at risk of progression.

Limitations of Use

- SYNJARDY and SYNJARDY XR are not recommended for use to improve glycemic control in patients with type 1 diabetes mellitus. It may increase the risk of diabetic ketoacidosis in these patients [see Warnings and Precautions (5.2)].
- Because of the metformin HCl component, the use of SYNJARDY or SYNJARDY XR is limited to patients with type 2 diabetes mellitus for all indications.
- Empagliflozin, when used as a component of SYNJARDY or SYNJARDY XR, is not recommended for the treatment of chronic kidney disease in patients with polycystic kidney disease or patients requiring or with a recent history of intravenous immunosuppressive therapy or greater than 45 mg of prednisone or equivalent for kidney disease [see Clinical Studies (14.5)]. Empagliflozin is not expected to be effective in these populations.

2 DOSAGE AND ADMINISTRATION

2.1 Testing Prior to Initiation of SYNJARDY or SYNJARDY XR

- Assess renal function before initiating SYNJARDY or SYNJARDY XR and as clinically indicated [see Warnings and Precautions (5.1, 5.3)].
- Assess volume status. In patients with volume depletion, correct this condition before initiating SYNJARDY or SYNJARDY XR [see Warnings and Precautions (5.3) and Use in Specific Populations (8.5, 8.6)].

2.2 Recommended Dosage and Administration of SYNJARDY or SYNJARDY XR in Adults

- When switching to SYNJARDY or SYNJARDY XR from:
  - Metformin HCl: initiate SYNJARDY or SYNJARDY XR at a similar total daily dosage of metformin HCl and a total daily empagliflozin dosage of 10 mg.
  - Empagliflozin: initiate SYNJARDY or SYNJARDY XR at the same total daily dosage of empagliflozin and a total daily metformin HCl dosage of 1,000 mg.
  - Empagliflozin and metformin HCl: initiate SYNJARDY or SYNJARDY XR at the same total daily dosages of each component.
- Recommended dosage of SYNJARDY or SYNJARDY XR:
  - The recommended total daily dosage of empagliflozin is 10 mg.
  - For additional glycemic control, empagliflozin may be increased to a maximum total daily dosage of 25 mg in patients tolerating 10 mg daily and metformin HCl may be increased to a maximum total daily dosage of 2,000 mg, with gradual escalation to reduce gastrointestinal adverse reactions with metformin HCl [see Adverse Reactions (6.1)].
- Take SYNJARDY orally twice daily with meals.
- Take SYNJARDY XR orally once daily with a meal in the morning. Swallow each tablet whole. Do not split, crush, dissolve, or chew.

2.3 Recommended Dosage and Administration of SYNJARDY in Pediatric Patients Aged 10 Years and Older

- Individualize the dosage of SYNJARDY based on the patient's current regimen.
- Monitor effectiveness and tolerability, and adjust dosage as appropriate, not to exceed the maximum total daily dosage of empagliflozin 25 mg and metformin HCl 2,000 mg.
- Take SYNJARDY orally twice daily with meals; with gradual dose escalation to reduce gastrointestinal adverse reactions with metformin HCl [see Adverse Reactions (6.1)].

2.4 Dosage Recommendations in Patients with Renal Impairment

- Initiation of SYNJARDY or SYNJARDY XR is not recommended in patients with an eGFR less than 45 mL/min/1.73 m^2, due to the metformin HCl component.
- SYNJARDY and SYNJARDY XR are contraindicated in patients with an eGFR less than 30 mL/min/1.73 m^2 [see Contraindications (4), Warnings and Precautions (5.1), and Use in Specific Populations (8.6)].

2.5 Discontinuation for Iodinated Contrast Imaging Procedures

Discontinue SYNJARDY or SYNJARDY XR at the time of, or prior to, an iodinated contrast imaging procedure in patients with an eGFR less than 60 mL/min/1.73 m^2; in patients with a history of liver disease, alcoholism or heart failure; or in patients who will be administered intra-arterial iodinated contrast. Re-evaluate eGFR 48 hours after the imaging procedure; restart SYNJARDY or SYNJARDY XR if renal function is stable [see Warnings and Precautions (5.1)].

2.6 Temporary Interruption for Surgery

Withhold SYNJARDY or SYNJARDY XR for at least 3 days, if possible, prior to surgery or procedures associated with prolonged fasting. Resume SYNJARDY or SYNJARDY XR when the patient is clinically stable and has resumed oral intake [see Warnings and Precautions (5.2) and Clinical Pharmacology (12.2)].

2.7 Recommendations Regarding Missed Dose

- If a dose is missed, instruct patients to take the dose as soon as possible.
- Advise patients not to double up the next dose.

3 DOSAGE FORMS AND STRENGTHS

SYNJARDY Tablets:

Empagliflozin Strength | Metformin HCl Strength | Color/Shape | Tablet Markings
5 mg | 500 mg | orange yellow, oval, biconvex, film-coated tablet | Boehringer Ingelheim company symbol and "S5" debossed on one side; the other side is debossed with "500".
5 mg | 1,000 mg | brownish yellow, oval, biconvex, film-coated tablet | Boehringer Ingelheim company symbol and "S5" debossed on one side; the other side is debossed with "1000".
12.5 mg | 500 mg | pale brownish purple, oval, biconvex, film-coated tablet | Boehringer Ingelheim company symbol and "S12" debossed on one side; the other side is debossed with "500".
12.5 mg | 1,000 mg | dark brownish purple, oval, biconvex, film-coated tablet | Boehringer Ingelheim company symbol and "S12" debossed on one side; the other side is debossed with "1000".

SYNJARDY XR Tablets:

Empagliflozin Strength | Metformin HCl Extended - Release Strength | Color/Shape | Tablet Markings
5 mg | 1,000 mg | olive green, oval, biconvex, film-coated tablet | Printed on one side in black ink with the Boehringer Ingelheim company symbol and "S5" on the top line and "1000 M" on the bottom line.
10 mg | 1,000 mg | orange, oval, biconvex, film-coated tablet | Printed on one side in black ink with the Boehringer Ingelheim company symbol and "S10" on the top line and "1000 M" on the bottom line.
12.5 mg | 1,000 mg | blue, oval, biconvex, film-coated tablet | Printed on one side in black ink with the Boehringer Ingelheim company symbol and "S12" on the top line and "1000 M" on the bottom line.
25 mg | 1,000 mg | light green, oval, biconvex, film-coated tablet | Printed on one side in black ink with the Boehringer Ingelheim company symbol and "S25" on the top line and "1000 M" on the bottom line.

4 CONTRAINDICATIONS

SYNJARDY and SYNJARDY XR are contraindicated in patients with:

- severe renal impairment (eGFR less than 30 mL/min/1.73 m^2) [see Warnings and Precautions (5.1) and Use in Specific Populations (8.6)].
- acute or chronic metabolic acidosis, including diabetic ketoacidosis [see Warnings and Precautions (5.1)].
- hypersensitivity to empagliflozin, metformin HCl or any of the excipients in SYNJARDY or SYNJARDY XR, reactions such as angioedema have occurred [see Warnings and Precautions (5.7)].

5 WARNINGS AND PRECAUTIONS

5.1 Lactic Acidosis

There have been postmarketing cases of metformin-associated lactic acidosis, including fatal cases. These cases had a subtle onset and were accompanied by nonspecific symptoms such as malaise, myalgias, abdominal pain, respiratory distress, or increased somnolence; however, hypothermia, hypotension, and resistant bradyarrhythmias have occurred with severe acidosis. Metformin-associated lactic acidosis was characterized by elevated blood lactate concentrations (>5 mmol/Liter), anion gap acidosis (without evidence of ketonuria or ketonemia), and an increased lactate:pyruvate ratio; metformin plasma levels generally >5 mcg/mL. Metformin decreases liver uptake of lactate increasing lactate blood levels which may increase the risk of lactic acidosis, especially in patients at risk.

If metformin-associated lactic acidosis is suspected, general supportive measures should be instituted promptly in a hospital setting, along with immediate discontinuation of SYNJARDY or SYNJARDY XR. In SYNJARDY or SYNJARDY XR-treated patients with a diagnosis or strong suspicion of lactic acidosis, prompt hemodialysis is recommended to correct the acidosis and remove accumulated metformin (metformin is dialyzable, with a clearance of up to 170 mL/minute under good hemodynamic conditions). Hemodialysis has often resulted in reversal of symptoms and recovery.

Educate patients and their families about the symptoms of lactic acidosis and if these symptoms occur instruct them to discontinue SYNJARDY or SYNJARDY XR and report these symptoms to their healthcare provider.

For each of the known and possible risk factors for metformin-associated lactic acidosis, recommendations to reduce the risk of and manage metformin-associated lactic acidosis are provided below:

Renal Impairment: The postmarketing metformin-associated lactic acidosis cases primarily occurred in patients with significant renal impairment. The risk of metformin accumulation and metformin-associated lactic acidosis increases with the severity of renal impairment because metformin is substantially excreted by the kidney. Clinical recommendations based upon the patient's renal function include [see Dosage and Administration (2.4) and Clinical Pharmacology (12.3)]:

- Before initiating SYNJARDY or SYNJARDY XR, obtain an estimated glomerular filtration rate (eGFR).
- SYNJARDY and SYNJARDY XR are contraindicated in patients with an eGFR below 30 mL/min/1.73 m^2 [see Contraindications (4)].
- Obtain an eGFR at least annually in all patients taking SYNJARDY or SYNJARDY XR. In patients at increased risk for the development of renal impairment (e.g., the elderly), renal function should be assessed more frequently.

Drug Interactions: The concomitant use of SYNJARDY or SYNJARDY XR with specific drugs may increase the risk of metformin-associated lactic acidosis: those that impair renal function, result in significant hemodynamic change, interfere with acid-base balance or increase metformin accumulation [see Drug Interactions (7)]. Therefore, consider more frequent monitoring of patients.

Age 65 or Greater: The risk of metformin-associated lactic acidosis increases with the patient's age because elderly patients have a greater likelihood of having hepatic, renal, or cardiac impairment than younger patients. Assess renal function more frequently in elderly patients [see Use in Specific Populations (8.5)].

Radiological Studies with Contrast: Administration of intravascular iodinated contrast agents in metformin-treated patients has led to an acute decrease in renal function and the occurrence of lactic acidosis. Stop SYNJARDY or SYNJARDY XR at the time of, or prior to, an iodinated contrast imaging procedure in patients with an eGFR less than 60 mL/min/1.73 m^2; in patients with a history of hepatic impairment, alcoholism, or heart failure; or in patients who will be administered intra-arterial iodinated contrast. Re-evaluate eGFR 48 hours after the imaging procedure, and restart SYNJARDY or SYNJARDY XR if renal function is stable.

Surgery and Other Procedures: Withholding of food and fluids during surgical or other procedures may increase the risk for volume depletion, hypotension and renal impairment. SYNJARDY or SYNJARDY XR should be temporarily discontinued while patients have restricted food and fluid intake.

Hypoxic States: Several of the postmarketing cases of metformin-associated lactic acidosis occurred in the setting of acute congestive heart failure (particularly when accompanied by hypoperfusion and hypoxemia). Cardiovascular collapse (shock), acute myocardial infarction, sepsis, and other conditions associated with hypoxemia have been associated with lactic acidosis and may also cause prerenal azotemia. When such events occur, discontinue SYNJARDY or SYNJARDY XR.

Excessive Alcohol Intake: Alcohol potentiates the effect of metformin on lactate metabolism and this may increase the risk of metformin-associated lactic acidosis. Warn patients against excessive alcohol intake while receiving SYNJARDY or SYNJARDY XR.

Hepatic Impairment: Patients with hepatic impairment have developed cases of metformin-associated lactic acidosis. This may be due to impaired lactate clearance resulting in higher lactate blood levels. Therefore, avoid use of SYNJARDY or SYNJARDY XR in patients with clinical or laboratory evidence of hepatic disease.

5.2 Diabetic Ketoacidosis in Patients with Type 1 Diabetes Mellitus and Other Ketoacidosis

In patients with type 1 diabetes mellitus, empagliflozin, a component of SYNJARDY or SYNJARDY XR, significantly increases the risk of diabetic ketoacidosis, a life-threatening event, beyond the background rate. In placebo-controlled trials of patients with type 1 diabetes mellitus, the risk of ketoacidosis was markedly increased in patients who received sodium glucose co-transporter 2 (SGLT2) inhibitors compared to patients who received placebo and fatal ketoacidosis has occurred with empagliflozin. SYNJARDY and SYNJARDY XR are not indicated for glycemic control in patients with type 1 diabetes mellitus.

Type 2 diabetes mellitus and pancreatic disorders (e.g., history of pancreatitis or pancreatic surgery) are also risk factors for ketoacidosis. There have been postmarketing reports of fatal events of ketoacidosis in patients with type 2 diabetes mellitus using SGLT2 inhibitors, including SYNJARDY or SYNJARDY XR.

Precipitating conditions for diabetic ketoacidosis or other ketoacidosis include under-insulinization due to insulin dose reduction or missed insulin doses, acute febrile illness, reduced caloric intake, ketogenic diet, surgery, volume depletion, and alcohol abuse.

Signs and symptoms are consistent with dehydration and severe metabolic acidosis and include nausea, vomiting, abdominal pain, generalized malaise, and shortness of breath. Blood glucose levels at presentation may be below those typically expected for diabetic ketoacidosis (e.g., less than 250 mg/dL). Ketoacidosis and glucosuria may persist longer than typically expected. Urinary glucose excretion persists for 3 days after discontinuing SYNJARDY or SYNJARDY XR [see Clinical Pharmacology (12.2)]; however, there have been postmarketing reports of ketoacidosis and/or glucosuria lasting greater than 6 days and some up to 2 weeks after discontinuation of SGLT2 inhibitors.

Consider ketone monitoring in patients at risk for ketoacidosis if indicated by the clinical situation. Assess for ketoacidosis regardless of presenting blood glucose levels in patients who present with signs and symptoms consistent with severe metabolic acidosis. If ketoacidosis is suspected, discontinue SYNJARDY or SYNJARDY XR, promptly evaluate, and treat ketoacidosis, if confirmed. Monitor patients for resolution of ketoacidosis before restarting SYNJARDY or SYNJARDY XR.

Withhold SYNJARDY or SYNJARDY XR, if possible, in temporary clinical situations that could predispose patients to ketoacidosis. Resume SYNJARDY or SYNJARDY XR when the patient is clinically stable and has resumed oral intake [see Dosage and Administration (2.6)].

Educate all patients on the signs and symptoms of ketoacidosis and instruct patients to discontinue SYNJARDY or SYNJARDY XR and seek medical attention immediately if signs and symptoms occur.

5.3 Volume Depletion

Empagliflozin can cause intravascular volume depletion which may sometimes manifest as symptomatic hypotension or acute transient changes in creatinine [see Adverse Reactions (6.1)]. There have been post-marketing reports of acute kidney injury, some requiring hospitalization and dialysis, in patients with type 2 diabetes mellitus receiving SGLT2 inhibitors, including empagliflozin. Patients with impaired renal function (eGFR less than 60 mL/min/1.73 m^2), elderly patients, or patients on loop diuretics may be at increased risk for volume depletion or hypotension. Before initiating SYNJARDY or SYNJARDY XR in patients with one or more of these characteristics, assess volume status and renal function. In patients with volume depletion, correct this condition before initiating SYNJARDY or SYNJARDY XR. Monitor for signs and symptoms of volume depletion, and renal function after initiating therapy.

5.4 Genitourinary Infections, including Urosepsis, Pyelonephritis, Necrotizing Fasciitis of the Perineum (Fournier's Gangrene), and Genital Mycotic Infections

Empagliflozin increases urinary glucose excretion [see Clinical Pharmacology (12.2)] and increases the risk of genitourinary infections including urinary tract infections and genital mycotic infections in both male and female patients [see Adverse Reactions (6.1)].

Serious genitourinary infections, including urosepsis, pyelonephritis, and necrotizing fasciitis of the perineum (Fournier's gangrene, a rare life-threatening infection requiring urgent surgical intervention), have occurred in patients with and without diabetes mellitus receiving SGLT2 inhibitors, including empagliflozin [see Adverse Reactions (6.2)]. Cases have required hospitalization. In patients with Fournier's gangrene, serious outcomes have included multiple surgeries and death. SYNJARDY and SYNJARDY XR are only indicated for use in patients with type 2 diabetes mellitus.

Patients with a history of chronic or recurrent genitourinary infections are more likely to develop genitourinary infections when using SYNJARDY or SYNJARDY XR. Monitor patients for signs and symptoms of genitourinary infections and treat promptly, if indicated.

Immediately evaluate patients presenting with pain or tenderness, erythema, or swelling in the genital or perineal area, along with fever or malaise, for necrotizing fasciitis. If suspected, discontinue SYNJARDY or SYNJARDY XR and promptly institute appropriate medical and/or surgical intervention.

5.5 Hypoglycemia

Insulin and insulin secretagogues are known to cause hypoglycemia. In adult patients, the risk of hypoglycemia may be increased when SYNJARDY or SYNJARDY XR is used in combination with insulin secretagogues (e.g., sulfonylurea) or insulin. In pediatric patients aged 10 years and older, the risk of hypoglycemia was higher with empagliflozin regardless of insulin use [see Adverse Reactions (6.1)].

The risk of hypoglycemia may be lowered by a reduction in the dose of sulfonylurea (or other concomitantly administered insulin secretagogues) or insulin. Inform patients using these concomitant medications and pediatric patients of the risk of hypoglycemia and educate them on the signs and symptoms of hypoglycemia.

5.6 Lower Limb Amputation

In some clinical studies with SGLT2 inhibitors an imbalance in the incidence of lower limb amputation has been observed. Across four empagliflozin outcome trials, lower limb amputation event rates were 4.3 and 5.0 events per 1,000 patient-years in the placebo group and the empagliflozin 10 mg or 25 mg dose group, respectively, with a HR of 1.05 (95% CI) (0.81, 1.36).

In a long-term cardio-renal outcome trial with empagliflozin, in patients with chronic kidney disease, the occurrence of lower limb amputations was reported with event rates of 2.9, and 4.3 events per 1,000 patient-years in the placebo, and empagliflozin 10 mg treatment arms, respectively. Amputation of the toe and mid-foot were most frequent (21 out of 28 empagliflozin 10 mg treated patients with lower limb amputations), and some involving above and below the knee. Some patients had multiple amputations.

Peripheral artery disease, and diabetic foot infection (including osteomyelitis), were the most common precipitating medical events leading to the need for an amputation. The risk of amputation was highest in patients with a baseline history of diabetic foot, peripheral artery disease (including previous amputation) or diabetes.

Counsel patients about the importance of routine preventative foot care. Monitor patients receiving SYNJARDY or SYNJARDY XR for signs and symptoms of diabetic foot infection (including osteomyelitis), new pain or tenderness, sores or ulcers involving the lower limbs, and institute appropriate treatment.

5.7 Hypersensitivity Reactions

There have been postmarketing reports of serious hypersensitivity reactions (e.g., angioedema) in patients treated with empagliflozin. If a hypersensitivity reaction occurs, discontinue SYNJARDY or SYNJARDY XR; treat promptly per standard of care, and monitor until signs and symptoms resolve. SYNJARDY and SYNJARDY XR are contraindicated in patients with hypersensitivity to empagliflozin or any of the excipients in SYNJARDY or SYNJARDY XR [see Contraindications (4)].

5.8 Vitamin B12 Deficiency

In metformin HCl clinical trials of 29-week duration, a decrease to subnormal levels of previously normal serum vitamin B12 levels was observed in approximately 7% of metformin-treated patients. Such decrease, possibly due to interference with B12 absorption from the B12-intrinsic factor complex, may be associated with anemia but appears to be rapidly reversible with discontinuation of metformin or vitamin B12 supplementation. Certain individuals (those with inadequate vitamin B12 or calcium intake or absorption) appear to be predisposed to developing subnormal vitamin B12 levels. Measure hematologic parameters on an annual basis and vitamin B12 at 2 to 3 year intervals in patients on SYNJARDY or SYNJARDY XR and manage any abnormalities [see Adverse Reactions (6.1)].

6 ADVERSE REACTIONS

The following important adverse reactions are described below and elsewhere in the labeling:

- Lactic Acidosis [see Boxed Warning and Warnings and Precautions (5.1)]
- Diabetic Ketoacidosis in Patients with Type 1 Diabetes Mellitus and Other Ketoacidosis [see Warnings and Precautions (5.2)]
- Volume Depletion [see Warnings and Precautions (5.3)]
- Genitourinary Infections, including Urosepsis, Pyelonephritis, Necrotizing Fasciitis of the Perineum (Fournier's Gangrene), and Genital Mycotic Infections [see Warnings and Precautions (5.4)]
- Hypoglycemia [see Warnings and Precautions (5.5)]
- Lower Limb Amputation [see Warnings and Precautions (5.6)]
- Hypersensitivity Reactions [see Warnings and Precautions (5.7)]
- Vitamin B12 Deficiency [see Warnings and Precautions (5.8)]

6.1 Clinical Trials Experience

Because clinical trials are conducted under widely varying conditions, adverse reaction rates observed in the clinical trials of a drug cannot be directly compared to rates in the clinical trials of another drug and may not reflect the rates observed in practice.

The safety of concomitantly administered empagliflozin (daily dosage 10 mg or 25 mg) and metformin HCl (mean daily dosage of approximately 1,800 mg) has been evaluated in 3,456 adult patients with type 2 diabetes mellitus treated for 16 to 24 weeks, of which 926 patients received placebo, 1,271 patients received a daily dosage of empagliflozin 10 mg, and 1,259 patients received a daily dosage of empagliflozin 25 mg. Discontinuation of therapy due to adverse events across treatment groups was 3.0%, 2.8%, and 2.9% for placebo, empagliflozin 10 mg, and empagliflozin 25 mg, respectively.

Adverse Reactions in a Clinical Trial with Empagliflozin (Add-On Combination Therapy with Metformin HCl and Sulfonylurea) for Glycemic Control in Adults with Type 2 Diabetes Mellitus

In a 24-week placebo-controlled trial of empagliflozin 10 mg or 25 mg administered once daily added to metformin HCl and sulfonylurea, adverse reactions reported in ≥5% of empagliflozin-treated patients and more commonly than in placebo-treated patients are presented in Table 1 (see also Table 4).

Table 1 Adverse Reactions Reported in ≥5% of Adults with Type 2 Diabetes Mellitus Treated with Empagliflozin added on to Metformin HCl plus Sulfonylurea and Greater than with Placebo in a 24-week Placebo Controlled Clinical Trial
Adverse Reactions | Placebo (%) n=225 | Empagliflozin 10 mg (%) n=224 | Empagliflozin 25 mg (%) n=217
Hypoglycemia | 9.8 | 15.6 | 12.9
Urinary tract infection | 6.7 | 9.4 | 6.9
Nasopharyngitis | 4.9 | 8.0 | 6.0

Empagliflozin

Clinical Trials in Adults with Type 2 Diabetes Mellitus

The data in Table 2 are derived from a pool of four 24-week placebo-controlled trials and 18-week data from a placebo-controlled trial with basal insulin in adult patients with type 2 diabetes mellitus. Empagliflozin was used as monotherapy in one trial and as add-on therapy in four trials [see Clinical Studies (14.1)].

These data reflect exposure of 1,976 adult patients to empagliflozin with a mean exposure duration of approximately 23 weeks. Patients received placebo (N=995), empagliflozin 10 mg (N=999), or empagliflozin 25 mg (N=977) once daily. The mean age of the population was 56 years and 3% were older than 75 years of age. More than half (55%) of the population was male; 46% were White, 50% were Asian, and 3% were Black or African American. At baseline, 57% of the population had diabetes mellitus more than 5 years and had a mean hemoglobin A1c (HbA1c) of 8%. Established microvascular complications of diabetes mellitus at baseline included diabetic nephropathy (7%), retinopathy (8%), or neuropathy (16%). Baseline renal function was normal or mildly impaired in 91% of patients and moderately impaired in 9% of patients (mean eGFR 86.8 mL/min/1.73 m^2).

Table 2 shows adverse reactions (excluding hypoglycemia) that were not present at baseline, occurred more commonly in empagliflozin-treated patients than placebo-treated patients, and occurred in greater than or equal to 2% of empagliflozin-treated patients.

Table 2 Adverse Reactions Reported in ≥2% of Adults with Type 2 Diabetes Mellitus Treated with Empagliflozin and Greater than Placebo in Pooled Placebo-Controlled Clinical Trials of Empagliflozin Monotherapy or Combination Therapy
Adverse Reactions | Placebo (%) N=995 | Empagliflozin 10 mg (%) N=999 | Empagliflozin 25 mg (%) N=977
Urinary tract infectiona | 7.6 | 9.3 | 7.6
Female genital mycotic infectionsb | 1.5 | 5.4 | 6.4
Upper respiratory tract infection | 3.8 | 3.1 | 4.0
Increased urinationc | 1.0 | 3.4 | 3.2
Dyslipidemia | 3.4 | 3.9 | 2.9
Arthralgia | 2.2 | 2.4 | 2.3
Male genital mycotic infectionsd | 0.4 | 3.1 | 1.6
Nausea | 1.4 | 2.3 | 1.1
aPredefined adverse event grouping, including, but not limited to, urinary tract infection, asymptomatic bacteriuria, cystitis
bFemale genital mycotic infections include the following adverse reactions: vulvovaginal mycotic infection, vaginal infection, vulvitis, vulvovaginal candidiasis, genital infection, genital candidiasis, genital infection fungal, genitourinary tract infection, vulvovaginitis, cervicitis, urogenital infection fungal, vaginitis bacterial. Percentages calculated with the number of female subjects in each group as denominator: placebo (N=481), empagliflozin 10 mg (N=443), empagliflozin 25 mg (N=420).
cPredefined adverse event grouping, including, but not limited to, polyuria, pollakiuria, and nocturia
dMale genital mycotic infections include the following adverse reactions: balanoposthitis, balanitis, genital infections fungal, genitourinary tract infection, balanitis candida, scrotal abscess, penile infection. Percentages calculated with the number of male subjects in each group as denominator: placebo (N=514), empagliflozin 10 mg (N=556), empagliflozin 25 mg (N=557).

Thirst (including polydipsia) was reported in 0%, 1.7%, and 1.5% for placebo, empagliflozin 10 mg, and empagliflozin 25 mg, respectively.

Volume Depletion

Empagliflozin causes an osmotic diuresis, which may lead to intravascular volume contraction and adverse reactions related to volume depletion. In the pool of five placebo-controlled clinical trials in adults, adverse reactions related to volume depletion (e.g., blood pressure (ambulatory) decreased, blood pressure systolic decreased, dehydration, hypotension, hypovolemia, orthostatic hypotension, and syncope) were reported by 0.3%, 0.5%, and 0.3% of patients treated with placebo, empagliflozin 10 mg, and empagliflozin 25 mg, respectively. Empagliflozin may increase the risk of hypotension in patients at risk for volume contraction [see Use in Specific Populations (8.5, 8.6)].

Increased Urination

In the pool of five placebo-controlled clinical trials in adults, adverse reactions of increased urination (e.g., polyuria, pollakiuria, and nocturia) occurred more frequently on empagliflozin than on placebo (see Table 2). Specifically, nocturia was reported by 0.4%, 0.3%, and 0.8% of patients treated with placebo, empagliflozin 10 mg, and empagliflozin 25 mg, respectively.

Hypoglycemia in Clinical Trials with Empagliflozin for Glycemic Control in Adults with Type 2 Diabetes Mellitus

The incidence of hypoglycemia in adults by trial is shown in Table 3. The incidence of hypoglycemia increased when empagliflozin was administered with insulin or sulfonylurea.

Table 3 Incidence of Overalla and Severeb Hypoglycemic Events in Placebo-Controlled Clinical Trials for Glycemic Control in Adults with Type 2 Diabetes Mellitusc
Monotherapy (24 weeks) | Placebo (n=229) | Empagliflozin 10 mg (n=224) | Empagliflozin 25 mg (n=223)
Overall (%) | 0.4 | 0.4 | 0.4
Severe (%) | 0 | 0 | 0
In Combination with Metformin HCl (24 weeks) | Placebo + Metformin HCl (n=206) | Empagliflozin 10 mg + Metformin HCl (n=217) | Empagliflozin 25 mg + Metformin HCl (n=214)
Overall (%) | 0.5 | 1.8 | 1.4
Severe (%) | 0 | 0 | 0
In Combination with Metformin HCl + Sulfonylurea (24 weeks) | Placebo (n=225) | Empagliflozin 10 mg + Metformin HCl + Sulfonylurea (n=224) | Empagliflozin 25 mg + Metformin HCl + Sulfonylurea (n=217)
Overall (%) | 8.4 | 16.1 | 11.5
Severe (%) | 0 | 0 | 0
In Combination with Pioglitazone +/- Metformin HCl (24 weeks) | Placebo (n=165) | Empagliflozin 10 mg + Pioglitazone +/- Metformin HCl (n=165) | Empagliflozin 25 mg + Pioglitazone +/- Metformin HCl (n=168)
Overall (%) | 1.8 | 1.2 | 2.4
Severe (%) | 0 | 0 | 0
In Combination with Basal Insulin +/- Metformin HCl (18 weeksd) | Placebo (n=170) | Empagliflozin 10 mg (n=169) | Empagliflozin 25 mg (n=155)
Overall (%) | 20.6 | 19.5 | 28.4
Severe (%) | 0 | 0 | 1.3
In Combination with MDI Insulin +/- Metformin HCl (18 weeksd) | Placebo (n=188) | Empagliflozin 10 mg (n=186) | Empagliflozin 25 mg (n=189)
Overall (%) | 37.2 | 39.8 | 41.3
Severe (%) | 0.5 | 0.5 | 0.5
aOverall hypoglycemic events: plasma or capillary glucose of less than or equal to 70 mg/dL
bSevere hypoglycemic events: requiring assistance regardless of blood glucose
cTreated set (patients who had received at least one dosage of trial drug)
dInsulin dosage could not be adjusted during the initial 18-week treatment period

Other Adverse Reactions in Clinical Trials with Empagliflozin in Adults

- Genital Mycotic Infections: In the pool of five placebo-controlled clinical trials, the incidence of genital mycotic infections (e.g., vaginal mycotic infection, vaginal infection, genital infection fungal, vulvovaginal candidiasis, and vulvitis) was increased in patients treated with empagliflozin compared to placebo, occurring in 0.9%, 4.1%, and 3.7% of patients randomized to placebo, empagliflozin 10 mg, and empagliflozin 25 mg, respectively. Discontinuation from trial due to genital infection occurred in 0% of placebo-treated patients and 0.2% of patients treated with either empagliflozin 10 mg or 25 mg.
  Genital mycotic infections occurred more frequently in female than male patients (see Table 2).
  Phimosis occurred more frequently in male patients treated with empagliflozin 10 mg (less than 0.1%) and empagliflozin 25 mg (0.1%) than placebo (0%).
- Urinary Tract Infections: In the pool of five placebo-controlled clinical trials, the incidence of urinary tract infections (e.g., urinary tract infection, asymptomatic bacteriuria, and cystitis) was increased in patients treated with empagliflozin compared to placebo (see Table 2). Patients with a history of chronic or recurrent urinary tract infections were more likely to experience a urinary tract infection. The rate of treatment discontinuation due to urinary tract infections was 0.1%, 0.2%, and 0.1% for placebo, empagliflozin 10 mg, and empagliflozin 25 mg, respectively.
  Urinary tract infections occurred more frequently in female patients. The incidence of urinary tract infections in female patients randomized to placebo, empagliflozin 10 mg, and empagliflozin 25 mg was 16.6%, 18.4%, and 17.0%, respectively. The incidence of urinary tract infections in male patients randomized to placebo, empagliflozin 10 mg, and empagliflozin 25 mg was 3.2%, 3.6%, and 4.1%, respectively [see Use in Specific Populations (8.5)].
- Lower Limb Amputations: Across four empagliflozin outcome trials, lower limb amputation event rates were 4.3 and 5.0 events per 1,000 patient-years in the placebo group and the empagliflozin 10 mg or 25 mg dose group, respectively, with a HR of 1.05 (95% CI) (0.81, 1.36). In a long-term cardio-renal outcome trial with empagliflozin, in patients with chronic kidney disease, the occurrence of lower limb amputations was reported with event rates of 2.9, and 4.3 events per 1,000 patient-years in the placebo, and empagliflozin 10 mg treatment arms, respectively.

Clinical Trial of Empagliflozin in Pediatric Patients Aged 10 to 17 Years with Type 2 Diabetes Mellitus

Empagliflozin was administered to 52 patients in a trial of 157 pediatric patients aged 10 to 17 years with type 2 diabetes mellitus with a mean exposure to empagliflozin of 23.8 weeks [see Clinical Studies (14.2)]. Background therapies as adjunct to diet and exercise included metformin HCl (51%), a combination of metformin HCl and insulin (40.1%), insulin (3.2%), or none (5.7%). The mean HbA1c at baseline was 8.0% and the mean duration of type 2 diabetes mellitus was 2.1 years. The mean age was 14.5 years (range: 10-17 years) and 51.6% were aged 15 years and older. Approximately, 50% were White, 6% were Asian, 31% were Black or African American, and 38% were of Hispanic or Latino ethnicity. The mean BMI was 36.0 kg/m^2 and mean BMI Z-score was 3.0. Approximately 25% of the trial population had microalbuminuria or macroalbuminuria.

The risk of hypoglycemia was higher in pediatric patients treated with empagliflozin regardless of concomitant insulin use. Hypoglycemia, defined as a blood glucose <54 mg/dL, occurred in 10 (19.2%) patients and in 4 (7.5%) patients treated with empagliflozin and placebo, respectively. No severe hypoglycemic events occurred (severe hypoglycemia was defined as an event requiring the assistance of another person to actively administer carbohydrates, glucagon or take other corrective actions).

Adverse Reactions with Clinical Trials of Metformin HCl

The most common (>5%) established adverse reactions due to initiation of metformin HCl therapy are diarrhea, nausea/vomiting, flatulence, abdominal discomfort, indigestion, asthenia, and headache.

In a 24-week clinical trial in which extended-release metformin HCl or placebo was added to glyburide therapy, the most common (>5% and greater than placebo) adverse reactions in the combined treatment group were hypoglycemia (13.7% vs 4.9%), diarrhea (12.5% vs 5.6%), and nausea (6.7% vs 4.2%).

Pediatric Patients

In clinical trials with metformin HCl immediate-release tablets in pediatric patients with type 2 diabetes mellitus, the profile of adverse reactions was similar to that observed in adults.

Laboratory Test Abnormalities in Clinical Trials of Empagliflozin or Metformin HCl

Empagliflozin

- Increases in Serum Creatinine and Decreases in eGFR: Initiation of empagliflozin causes an increase in serum creatinine and decrease in eGFR within weeks of starting therapy and then these changes stabilize. In a trial of adults with moderate renal impairment, larger mean changes were observed. In a long-term CV outcomes trial, the increase in serum creatinine and decrease in eGFR generally did not exceed 0.1 mg/dL and -9.0 mL/min/1.73 m^2, respectively, at Week 4, and reversed after treatment discontinuation, suggesting acute hemodynamic changes may play a role in the renal function changes observed with empagliflozin.
- Increase in Low-Density Lipoprotein Cholesterol (LDL-C): Dose-related increases in low-density lipoprotein cholesterol (LDL-C) were observed in adults treated with empagliflozin. LDL-C increased by 2.3%, 4.6%, and 6.5% in patients treated with placebo, empagliflozin 10 mg, and empagliflozin 25 mg, respectively. The range of mean baseline LDL-C levels was 90.3 to 90.6 mg/dL across treatment groups.
- Increase in Hematocrit: In a pool of four placebo-controlled trials in adults, median hematocrit decreased by 1.3% in placebo and increased by 2.8% in empagliflozin 10 mg and 2.8% in empagliflozin 25 mg treated patients. At the end of treatment, 0.6%, 2.7%, and 3.5% of patients with hematocrits initially within the reference range had values above the upper limit of the reference range with placebo, empagliflozin 10 mg, and empagliflozin 25 mg, respectively.

Metformin HCl

- Decrease in Vitamin B12: In metformin HCl clinical trials of 29-week duration, a decrease to subnormal levels of previously normal serum vitamin B12 levels was observed in approximately 7% of patients.

6.2 Postmarketing Experience

Additional adverse reactions have been identified during postapproval use. Because these reactions are reported voluntarily from a population of uncertain size, it is generally not possible to reliably estimate their frequency or establish a causal relationship to drug exposure.

Empagliflozin

Gastrointestinal Disorders: Constipation
Infections: Necrotizing fasciitis of the perineum (Fournier's gangrene), urosepsis and pyelonephritis
Metabolism and Nutrition Disorders: Ketoacidosis
Renal and Urinary Disorders: Acute kidney injury
Skin and Subcutaneous Tissue Disorders: Angioedema, skin reactions (e.g., rash, urticaria)

Metformin HCl

Hepatobiliary Disorders: Cholestatic, hepatocellular, and mixed hepatocellular liver injury

7 DRUG INTERACTIONS

See Table 4 for clinically relevant interactions with SYNJARDY or SYNJARDY XR.

Table 4 Clinically Relevant Interactions with SYNJARDY or SYNJARDY XR
Carbonic Anhydrase Inhibitors
Clinical Impact | Topiramate or other carbonic anhydrase inhibitors (e.g., zonisamide, acetazolamide or dichlorphenamide) frequently causes a decrease in serum bicarbonate and induce non-anion gap, hyperchloremic metabolic acidosis. Concomitant use of these drugs with SYNJARDY or SYNJARDY XR may increase the risk of lactic acidosis.
Intervention | Consider more frequent monitoring of these patients.
Drugs that Reduce Metformin Clearance
Clinical Impact | Concomitant use of drugs that interfere with common renal tubular transport systems involved in the renal elimination of metformin (e.g., organic cationic transporter-2 [OCT2] / multidrug and toxin extrusion [MATE] inhibitors such as ranolazine, vandetanib, dolutegravir, and cimetidine) could increase systemic exposure to metformin and may increase the risk for lactic acidosis [see Clinical Pharmacology (12.3)].
Intervention | Consider the benefits and risks of concomitant use.
Alcohol
Clinical Impact | Alcohol is known to potentiate the effect of metformin on lactate metabolism.
Intervention | Warn patients against excessive alcohol intake while receiving SYNJARDY or SYNJARDY XR.
Diuretics
Clinical Impact | Coadministration of empagliflozin with diuretics resulted in increased urine volume and frequency of voids, which might enhance the potential for volume depletion.
Intervention | Before initiating SYNJARDY or SYNJARDY XR, assess volume status and renal function. In patients with volume depletion, correct this condition before initiating SYNJARDY or SYNJARDY XR. Monitor for signs and symptoms of volume depletion, and renal function after initiating therapy.
Insulin or Insulin Secretagogues
Clinical Impact | The risk of hypoglycemia is increased when SYNJARDY or SYNJARDY XR is used in combination with insulin secretagogues (e.g., sulfonylurea) or insulin.
Intervention | Coadministration of SYNJARDY or SYNJARDY XR with an insulin secretagogue (e.g., sulfonylurea) or insulin may require lower dosages of the insulin secretagogue or insulin to reduce the risk of hypoglycemia.
Drugs Affecting Glycemic Control
Clinical Impact | Certain drugs tend to produce hyperglycemia and may lead to loss of glycemic control. These drugs include the thiazides and other diuretics, corticosteroids, phenothiazines, thyroid products, estrogens, oral contraceptives, phenytoin, nicotinic acid, sympathomimetics, calcium channel blocking drugs, and isoniazid.
Intervention | When such drugs are administered to a patient receiving SYNJARDY or SYNJARDY XR, the patient should be closely observed to maintain adequate glycemic control. When such drugs are withdrawn from a patient receiving SYNJARDY or SYNJARDY XR, the patient should be observed closely for hypoglycemia.
Lithium
Clinical Impact | Concomitant use of an SGLT2 inhibitor with lithium may decrease serum lithium concentrations.
Intervention | Monitor serum lithium concentration more frequently during SYNJARDY or SYNJARDY XR initiation and dosage changes.
Positive Urine Glucose Test
Clinical Impact | SGLT2 inhibitors increase urinary glucose excretion and will lead to positive urine glucose tests.
Intervention | Monitoring glycemic control with urine glucose tests is not recommended in patients taking SGLT2 inhibitors. Use alternative methods to monitor glycemic control.
Interference with 1,5-anhydroglucitol (1,5-AG) Assay
Clinical Impact | Measurements of 1,5-AG are unreliable in assessing glycemic control in patients taking SGLT2 inhibitors.
Intervention | Monitoring glycemic control with 1,5-AG assay is not recommended. Use alternative methods to monitor glycemic control.

8 USE IN SPECIFIC POPULATIONS

8.1 Pregnancy

Risk Summary

Based on animal data showing adverse renal effects from empagliflozin, SYNJARDY and SYNJARDY XR are not recommended during the second and third trimesters of pregnancy.

The limited available data with SYNJARDY, SYNJARDY XR, or empagliflozin in pregnant women are not sufficient to determine a drug-associated risk for major birth defects and miscarriage. Published studies with metformin HCl use during pregnancy have not reported a clear association with metformin HCl and major birth defect or miscarriage risk (see Data). There are risks to the mother and fetus associated with poorly controlled diabetes in pregnancy (see Clinical Considerations).

In animal studies, empagliflozin, a component of SYNJARDY and SYNJARDY XR, resulted in adverse renal changes in rats when administered during a period of renal development corresponding to the late second and third trimesters of human pregnancy. Doses approximately 13-times the maximum clinical dose caused renal pelvic and tubule dilatations that were reversible. No adverse developmental effects were observed when metformin HCl was administered to pregnant rats or rabbits (see Data).

The estimated background risk of major birth defects is 6% to 10% in women with pre-gestational diabetes with a HbA1c >7 and has been reported to be as high as 20% to 25% in women with HbA1c >10. The estimated background risk of miscarriage for the indicated population is unknown. In the U.S. general population, the estimated background risk of major birth defects and miscarriage in clinically recognized pregnancies is 2% to 4% and 15% to 20%, respectively.

Clinical Considerations

Disease-associated maternal and/or embryo/fetal risk

Poorly controlled diabetes in pregnancy increases the maternal risk for diabetic ketoacidosis, pre-eclampsia, spontaneous abortions, preterm delivery, and delivery complications. Poorly controlled diabetes increases the fetal risk for major birth defects, stillbirth, and macrosomia related morbidity.

Data

Human Data

Published data from postmarketing studies have not reported a clear association with metformin HCl and major birth defects, miscarriage, or adverse maternal or fetal outcomes when metformin HCl was used during pregnancy. However, these studies cannot definitely establish the absence of any metformin-associated risk because of methodological limitations, including small sample size and inconsistent comparator groups.

Animal Data

Empagliflozin: Empagliflozin dosed directly to juvenile rats from postnatal day (PND) 21 until PND 90 at doses of 1, 10, 30, and 100 mg/kg/day caused increased kidney weights and renal tubular and pelvic dilatation at 100 mg/kg/day, which approximates 13-times the maximum clinical dose of 25 mg, based on AUC. These findings were not observed after a 13-week, drug-free recovery period. These outcomes occurred with drug exposure during periods of renal development in rats that correspond to the late second and third trimester of human renal development.

In embryo-fetal development studies in rats and rabbits, empagliflozin was administered for intervals coinciding with the first trimester period of organogenesis in humans. Doses up to 300 mg/kg/day, which approximates 48-times (rats) and 128-times (rabbits) the maximum clinical dose of 25 mg (based on AUC), did not result in adverse developmental effects. In rats, at higher doses of empagliflozin causing maternal toxicity, malformations of limb bones increased in fetuses at 700 mg/kg/day or 154-times the 25 mg maximum clinical dose. Empagliflozin crosses the placenta and reaches fetal tissues in rats. In the rabbit, higher doses of empagliflozin resulted in maternal and fetal toxicity at 700 mg/kg/day, or 139-times the 25 mg maximum clinical dose.

In pre- and postnatal development studies in pregnant rats, empagliflozin was administered from gestation day 6 through to lactation day 20 (weaning) at up to 100 mg/kg/day (approximately 16-times the 25 mg maximum clinical dose) without maternal toxicity. Reduced body weight was observed in the offspring at greater than or equal to 30 mg/kg/day (approximately 4-times the 25 mg maximum clinical dose).

Metformin HCl: Metformin HCl did not cause adverse developmental effects when administered to pregnant Sprague Dawley rats and rabbits at doses up to 600 mg/kg/day during the period of organogenesis. This represents an exposure of approximately 2- and 6-times a clinical dose of 2,000 mg, based on body surface area (mg/m^2) for rats and rabbits, respectively.

Empagliflozin and Metformin HCl: No adverse developmental effects were observed when empagliflozin and metformin HCl were coadministered to pregnant rats during the period of organogenesis at exposures of approximately 35- and 14-times the clinical AUC exposure of empagliflozin associated with the 10 mg and 25 mg doses, respectively, and 4-times the clinical AUC exposure of metformin HCl associated with the 2,000 mg dose.

8.2 Lactation

Risk Summary

There is limited information regarding the presence of SYNJARDY, SYNJARDY XR, or its components (empagliflozin or metformin HCl) in human milk, the effects on the breastfed infant, or the effects on milk production. Limited published studies report that metformin is present in human milk (see Data). Empagliflozin is present in the milk of lactating rats (see Data). Since human kidney maturation occurs in utero and during the first 2 years of life when lactational exposure may occur, there may be risk to the developing human kidney.

Because of the potential for serious adverse reactions in a breastfed infant, including the potential for empagliflozin to affect postnatal renal development, advise patients that use of SYNJARDY or SYNJARDY XR is not recommended while breastfeeding.

Data

Published clinical lactation studies report that metformin is present in human milk which resulted in infant doses approximately 0.11% to 1% of the maternal weight-adjusted dosage and a milk/plasma ratio ranging between 0.13 and 1. However, the studies were not designed to definitely establish the risk of use of metformin HCl during lactation because of small sample size and limited adverse event data collected in infants.

Empagliflozin was present at a low level in rat fetal tissues after a single oral dose to the dams at gestation day 18. In rat milk, the mean milk to plasma ratio ranged from 0.634 to 5, and was greater than one from 2 to 24 hours post-dose. The mean maximal milk to plasma ratio of 5 occurred at 8 hours post-dose, suggesting accumulation of empagliflozin in the milk. Juvenile rats directly exposed to empagliflozin showed a risk to the developing kidney (renal pelvic and tubular dilatations) during maturation.

8.3 Females and Males of Reproductive Potential

Discuss the potential for unintended pregnancy with premenopausal women as therapy with metformin HCl may result in ovulation in some anovulatory women.

8.4 Pediatric Use

SYNJARDY

The safety and effectiveness of SYNJARDY as an adjunct to diet and exercise to improve glycemic control in type 2 diabetes mellitus have been established in pediatric patients aged 10 years and older. Use of SYNJARDY for this indication is supported by evidence from a 26-week double-blind, placebo-controlled clinical trial of empagliflozin, with a double-blind active treatment safety extension period of up to 52 weeks in 157 pediatric patients aged 10 to 17 years with type 2 diabetes mellitus and a pediatric pharmacokinetic study [see Clinical Pharmacology (12.3) and Clinical Studies (14.2)].

The safety profile of pediatric patients treated with empagliflozin was similar to that observed in adults with type 2 diabetes mellitus, with the exception of hypoglycemia risk which was higher in pediatric patients treated with empagliflozin regardless of concomitant insulin use [see Warnings and Precautions (5.5) and Adverse Reactions (6.1)].

Use of SYNJARDY for this indication is also supported by evidence from adequate and well-controlled studies of metformin HCl immediate-release tablets in adults with additional data from a controlled clinical study using metformin HCl immediate-release tablets in pediatric patients 10 to 16 years old with type 2 diabetes mellitus [see Clinical Studies (14)]. In this study, adverse reactions were similar to those described in adults.

The safety and effectiveness of SYNJARDY have not been established in pediatric patients less than 10 years of age.

SYNJARDY XR

Safety and effectiveness of SYNJARDY XR have not been established in pediatric patients.

8.5 Geriatric Use

Assess renal function more frequently in SYNJARDY or SYNJARDY XR-treated geriatric patients because there is a greater risk of empagliflozin-associated intravascular volume contraction and symptomatic hypotension in geriatric patients and there is a greater risk of metformin-associated lactic acidosis in geriatric patients [see Dosage and Administration (2.4) and Warnings and Precautions (5.1, 5.3)].

The recommended dosage for the metformin HCl component of SYNJARDY or SYNJARDY XR in geriatric patients should usually start at the lower end of the dosage range.

Empagliflozin

In empagliflozin type 2 diabetes mellitus trials, 2,721 empagliflozin-treated patients were 65 years of age and older and 491 patients were 75 years of age and older. In these trials, volume depletion-related adverse reactions occurred in 2.1%, 2.3%, and 4.4% of patients 75 years of age and older in the placebo, empagliflozin 10 mg, and empagliflozin 25 mg once daily groups, respectively; and urinary tract infections occurred in 10.5%, 15.7%, and 15.1% of patients 75 years of age and older in the placebo, empagliflozin 10 mg, and empagliflozin 25 mg once daily groups, respectively.

In the EMPEROR-Reduced, EMPEROR-Preserved, and EMPA-KIDNEY trials, no overall differences in safety and effectiveness have been observed between patients 65 years of age and older and younger adult patients. EMPEROR-Reduced included 1,188 (64%) patients treated with empagliflozin 65 years of age and older, and 503 (27%) patients 75 years of age and older. EMPEROR-Preserved included 2,403 (80%) patients treated with empagliflozin 65 years of age and older, and 1,281 (43%) patients 75 years of age and older. EMPA-KIDNEY included 1,803 (55%) patients treated with empagliflozin 65 years of age and older, and 758 (23%) patients 75 years of age and older.

Metformin HCl

Clinical studies of metformin HCl did not include sufficient numbers of patients 65 years of age and older to determine whether they respond differently from younger adult patients.

8.6 Renal Impairment

SYNJARDY or SYNJARDY XR should not be initiated in patients with an eGFR less than 45 mL/min/1.73 m^2 due to the metformin HCl component and is contraindicated in patients with severe renal impairment (eGFR less than 30 mL/min/1.73 m^2).

Empagliflozin

The glucose lowering benefit of empagliflozin 25 mg decreased in adult patients with worsening renal function. The risks of renal impairment, volume depletion adverse reactions and urinary tract infection-related adverse reactions increased with worsening renal function [see Warnings and Precautions (5.3)]. In the trial of pediatric patients aged 10 to 17 years with type 2 diabetes mellitus, patients with an eGFR less than 60 mL/min/1.73 m^2 were not enrolled.

Metformin HCl

Metformin is substantially excreted by the kidney, and the risk of metformin accumulation and lactic acidosis increases with the degree of renal impairment [see Warnings and Precautions (5.1)].

8.7 Hepatic Impairment

Use of metformin HCl in patients with hepatic impairment has been associated with some cases of lactic acidosis. SYNJARDY and SYNJARDY XR are not recommended in patients with hepatic impairment [see Warnings and Precautions (5.1)].

10 OVERDOSAGE

In the event of an overdose with SYNJARDY or SYNJARDY XR, consider contacting the Poison Help line (1-800-222-1222) or a medical toxicologist for additional overdosage management recommendations.

Overdose of metformin HCl has occurred, including ingestion of amounts greater than 50 grams. Lactic acidosis has been reported in approximately 32% of metformin overdose cases [see Warnings and Precautions (5.1)]. Metformin is dialyzable with a clearance of up to 170 mL/min under good hemodynamic conditions. Therefore, hemodialysis may be useful for removal of accumulated drug from patients in whom metformin overdosage is suspected.

Removal of empagliflozin by hemodialysis has not been studied.

11 DESCRIPTION

SYNJARDY and SYNJARDY XR tablets for oral use contain: empagliflozin and metformin HCl.

Empagliflozin

Empagliflozin is an inhibitor of the SGLT2.

The chemical name of empagliflozin is D-Glucitol,1,5-anhydro-1-C-[4-chloro-3-[[4-[[(3S)-tetrahydro-3-furanyl]oxy]phenyl]methyl]phenyl]-, (1S).

Its molecular formula is C23H27ClO7 and the molecular weight is 450.91. The structural formula is:

Empagliflozin is a white to yellowish, non-hygroscopic powder. It is very slightly soluble in water, sparingly soluble in methanol, slightly soluble in ethanol and acetonitrile, soluble in 50% acetonitrile/water, and practically insoluble in toluene.

Metformin HCl

Metformin HCl (N,N-dimethylimidodicarbonimidic diamide HCl) is a biguanide. Metformin HCl is a white to off-white crystalline compound with a molecular formula of C4H11N5•HCl and a molecular weight of 165.63. Metformin HCl is freely soluble in water and is practically insoluble in acetone, ether, and chloroform. The pKa of metformin is 12.4. The pH of a 1% aqueous solution of metformin HCl is 6.68. The structural formula is:

SYNJARDY

SYNJARDY tablets for oral administration are available in four dosage strengths containing:

- 5 mg empagliflozin and 500 mg metformin HCl (equivalent to 389.93 mg of metformin)
- 5 mg empagliflozin and 1,000 mg metformin HCl (equivalent to 779.86 mg of metformin)
- 12.5 mg empagliflozin and 500 mg metformin HCl (equivalent to 389.93 mg of metformin)
- 12.5 mg empagliflozin and 1,000 mg metformin HCl (equivalent to 779.86 mg of metformin)

Each film-coated tablet of SYNJARDY contains the following inactive ingredients: colloidal silicon dioxide, copovidone, corn starch, and magnesium stearate. Film-coating: black ferrosoferric oxide and ferric oxide red (12.5 mg/500 mg, 12.5 mg/1,000 mg) or ferric oxide yellow (5 mg/500 mg, 5 mg/1,000 mg), hypromellose, polyethylene glycol 400, talc and titanium dioxide.

SYNJARDY XR

Each film-coated tablet of SYNJARDY XR consists of an extended-release metformin HCl core tablet that is coated with the immediate-release drug substance empagliflozin.

SYNJARDY XR tablets for oral administration are available in four dosage strengths containing:

- 5 mg empagliflozin and 1,000 mg metformin HCl (equivalent to 779.86 mg of metformin)
- 10 mg empagliflozin and 1,000 mg metformin HCl (equivalent to 779.86 mg of metformin)
- 12.5 mg empagliflozin and 1,000 mg metformin HCl (equivalent to 779.86 mg of metformin)
- 25 mg empagliflozin and 1,000 mg metformin HCl (equivalent to 779.86 mg of metformin)

Each film-coated tablet of SYNJARDY XR contains the following inactive ingredients: Tablet Core: hypromellose, magnesium stearate, and polyethylene oxide. Film-coatings and Printing Ink: carnauba wax, FD&C blue#2/indigo carmine aluminum lake (12.5 mg/1,000 mg, 25 mg/1,000 mg), ferric oxide red (10 mg/1,000 mg), ferric oxide yellow (5 mg/1,000 mg, 10 mg/1,000 mg, 25 mg/1,000 mg), ferrosoferric oxide, hypromellose, isopropyl alcohol, polydextrose, polyethylene glycol, propylene glycol, purified water, talc, and titanium dioxide.

12 CLINICAL PHARMACOLOGY

12.1 Mechanism of Action

SYNJARDY or SYNJARDY XR

SYNJARDY and SYNJARDY XR contain: empagliflozin, a SGLT2 inhibitor, and metformin HCl, a biguanide.

Empagliflozin

Empagliflozin is an inhibitor of SGLT2, the predominant transporter responsible for reabsorption of glucose from the glomerular filtrate back into the circulation. By inhibiting SGLT2, empagliflozin reduces renal reabsorption of filtered glucose and lowers the renal threshold for glucose, and thereby increases urinary glucose excretion.

Empagliflozin also reduces sodium reabsorption and increases the delivery of sodium to the distal tubule. This may influence several physiological functions including, but not restricted to, increasing tubuloglomerular feedback and reducing intraglomerular pressure, lowering both pre- and afterload of the heart and downregulating sympathetic activity.

Metformin HCl

Metformin HCl is an antihyperglycemic agent which improves glucose tolerance in patients with type 2 diabetes mellitus, lowering both basal and postprandial plasma glucose. It is not chemically or pharmacologically related to any other classes of oral antihyperglycemic agents. Metformin HCl decreases hepatic glucose production, decreases intestinal absorption of glucose, and improves insulin sensitivity by increasing peripheral glucose uptake and utilization. Unlike sulfonylureas, metformin HCl does not produce hypoglycemia in either patients with type 2 diabetes mellitus or normal subjects (except in special circumstances) [see Warnings and Precautions (5.5)] and does not cause hyperinsulinemia. With metformin HCl therapy, insulin secretion remains unchanged while fasting insulin levels and day-long plasma insulin response may decrease.

12.2 Pharmacodynamics

Empagliflozin

Urinary Glucose Excretion

In patients with type 2 diabetes mellitus, urinary glucose excretion increased immediately following a dose of empagliflozin and was maintained at the end of a 4-week treatment period averaging at approximately 64 grams per day with 10 mg empagliflozin and 78 grams per day with 25 mg empagliflozin once daily [see Clinical Studies (14)]. Data from single oral doses of empagliflozin in healthy subjects indicate that, on average, the elevation in urinary glucose excretion approaches baseline by about 3 days for the 10 mg and 25 mg doses.

Urinary Volume

In a 5-day study, mean 24-hour urine volume increase from baseline was 341 mL on Day 1 and 135 mL on Day 5 of empagliflozin 25 mg once daily treatment.

Cardiac Electrophysiology

In a randomized, placebo-controlled, active-comparator, crossover study, 30 healthy subjects were administered a single oral dose of empagliflozin 25 mg, empagliflozin 200 mg (8 times the maximum dose), moxifloxacin, and placebo. No increase in QTc was observed with either 25 mg or 200 mg empagliflozin.

12.3 Pharmacokinetics

SYNJARDY

Administration of 12.5 mg empagliflozin/1,000 mg metformin HCl under fed conditions resulted in a 9% decrease in AUC and a 28% decrease in Cmax for empagliflozin, when compared to fasted conditions. For metformin, AUC decreased by 12% and Cmax decreased by 26% compared to fasting conditions. The observed effect of food on empagliflozin and metformin is not considered to be clinically relevant.

SYNJARDY XR

Administration of SYNJARDY XR with food resulted in no change in overall exposure of empagliflozin. For metformin HCl extended-release high-fat meals increased systemic exposure to metformin (as measured by area-under-the-curve [AUC]) by approximately 70% relative to fasting, while Cmax is not affected. Meals prolonged Tmax by approximately 3 hours.

Empagliflozin

The pharmacokinetics of empagliflozin has been characterized in healthy volunteers and patients with type 2 diabetes mellitus and no clinically relevant differences were noted between the two populations. The steady-state mean plasma AUC and Cmax were 1,870 nmol∙h/L and 259 nmol/L, respectively, with 10 mg empagliflozin once daily treatment, and 4,740 nmol∙h/L and 687 nmol/L, respectively, with 25 mg empagliflozin once daily treatment. Systemic exposure of empagliflozin increased in a dose-proportional manner in the therapeutic dose range. Empagliflozin does not appear to have time-dependent pharmacokinetic characteristics. Following once-daily dosing, up to 22% accumulation, with respect to plasma AUC, was observed at steady-state.

Absorption

After oral administration, peak plasma concentrations of empagliflozin were reached at 1.5 hours post-dose. Administration of 25 mg empagliflozin after intake of a high-fat and high-calorie meal resulted in slightly lower exposure; AUC decreased by approximately 16% and Cmax decreased by approximately 37%, compared to fasted condition. The observed effect of food on empagliflozin pharmacokinetics was not considered clinically relevant and empagliflozin may be administered with or without food.

Distribution

The apparent steady-state volume of distribution was estimated to be 73.8 L based on a population pharmacokinetic analysis. Following administration of an oral [^14C]-empagliflozin solution to healthy subjects, the red blood cell partitioning was approximately 36.8% and plasma protein binding was 86.2%.

Elimination

The apparent terminal elimination half-life of empagliflozin was estimated to be 12.4 h and apparent oral clearance was 10.6 L/h based on the population pharmacokinetic analysis.

Metabolism

No major metabolites of empagliflozin were detected in human plasma and the most abundant metabolites were three glucuronide conjugates (2-O-, 3-O-, and 6-O-glucuronide). Systemic exposure of each metabolite was less than 10% of total drug-related material. In vitro studies suggested that the primary route of metabolism of empagliflozin in humans is glucuronidation by the uridine 5'-diphospho-glucuronosyltransferases UGT2B7, UGT1A3, UGT1A8, and UGT1A9.

Excretion

Following administration of an oral [^14C]-empagliflozin solution to healthy subjects, approximately 95.6% of the drug-related radioactivity was eliminated in feces (41.2%) or urine (54.4%). The majority of drug-related radioactivity recovered in feces was unchanged parent drug and approximately half of drug-related radioactivity excreted in urine was unchanged parent drug.

Metformin HCl

Absorption

The absolute bioavailability of a metformin HCl 500 mg tablet given under fasting conditions is approximately 50% to 60%. Studies using single oral doses of metformin HCl tablets 500 mg to 1,500 mg, and 850 mg to 2,550 mg, indicate that there is a lack of dose proportionality with increasing doses, which is due to decreased absorption rather than an alteration in elimination.

Food decreases the extent of and slightly delays the absorption of metformin, as shown by approximately a 40% lower Cmax, a 25% lower AUC, and a 35 minute prolongation of time to peak plasma concentration (Tmax) following administration of a single 850 mg tablet of metformin with food, compared to the same tablet strength administered fasting. The clinical relevance of these decreases is unknown.

Metformin HCl extended-release

Following a single oral dose of 1,000 mg (2 × 500 mg tablets) metformin HCl extended-release after a meal, the time to reach maximum plasma metformin concentration (Tmax) is achieved at approximately 7 to 8 hours. In both single- and multiple-dose studies in healthy subjects, once daily 1,000 mg (2 × 500 mg tablets) dosing provides equivalent systemic exposure, as measured by AUC, and up to 35% higher Cmax of metformin relative to the immediate-release given as 500 mg twice daily.

Single oral doses of metformin HCl extended-release from 500 mg to 2,500 mg resulted in less than proportional increase in both AUC and Cmax. Low-fat and high-fat meals increased the systemic exposure (as measured by AUC) from metformin extended-release tablets by about 38% and 73%, respectively, relative to fasting. Both meals prolonged metformin Tmax by approximately 3 hours but Cmax was not affected.

Distribution

The apparent volume of distribution (V/F) of metformin following single oral doses of immediate-release metformin HCl tablets 850 mg averaged 654±358 L. Metformin is negligibly bound to plasma proteins. Metformin partitions into erythrocytes, most likely as a function of time.

Elimination

Metformin has a plasma elimination half-life of approximately 6.2 hours. In blood, the elimination half-life is approximately 17.6 hours, suggesting that the erythrocyte mass may be a compartment of distribution.

Metabolism

Intravenous single-dose studies in normal subjects demonstrate that metformin does not undergo hepatic metabolism (no metabolites have been identified in humans) nor biliary excretion.

Excretion

Following oral administration, approximately 90% of the absorbed drug is excreted via the renal route within the first 24 hours. Renal clearance is approximately 3.5 times greater than creatinine clearance, which indicates that tubular secretion is the major route of metformin elimination.

Specific Populations

Geriatric Patients

SYNJARDY or SYNJARDY XR: Studies characterizing the pharmacokinetics of empagliflozin and metformin after administration of SYNJARDY or SYNJARDY XR in geriatric patients have not been performed [see Warnings and Precautions (5.2) and Use in Specific Populations (8.5)].

Empagliflozin: Age did not have a clinically meaningful impact on the pharmacokinetics of empagliflozin based on a population pharmacokinetic analysis [see Use in Specific Populations (8.5)].

Metformin HCl: Limited data from controlled pharmacokinetic studies of metformin HCl in healthy elderly subjects suggest that total plasma clearance of metformin is decreased, the half-life is prolonged, and Cmax is increased, compared with healthy young subjects. From these data, it appears that the change in metformin pharmacokinetics with aging is primarily accounted for by a change in renal function.

Pediatric Patients

Empagliflozin: The pharmacokinetics and pharmacodynamics of empagliflozin were investigated in pediatric patients aged 10 to 17 years with type 2 diabetes mellitus. Oral administration of empagliflozin at 10 mg and 25 mg resulted in exposure within the range observed in adult patients.

Metformin: After administration of a single oral metformin HCl 500 mg immediate-release tablet with food, geometric mean metformin Cmax and AUC differed less than 5% between pediatric type 2 diabetic patients (12 to 16 years of age) and gender- and weight-matched healthy adults (20 to 45 years of age), all with normal renal function.

Effects of Age, Body Mass Index, Gender, and Race

Empagliflozin: Age, body mass index (BMI), gender and race (Asians versus primarily Whites) do not have a clinically meaningful effect on pharmacokinetics of empagliflozin.

Metformin HCl: No studies of metformin pharmacokinetic parameters according to race have been performed. In controlled clinical studies of metformin HCl in patients with type 2 diabetes mellitus, the antihyperglycemic effect was comparable in Whites (n=249), Blacks or African Americans (n=51), and Hispanics or Latinos (n=24).

Patients with Renal Impairment

SYNJARDY or SYNJARDY XR: Studies characterizing the pharmacokinetics of empagliflozin and metformin HCl after administration of SYNJARDY or SYNJARDY XR in renally impaired patients have not been performed.

Empagliflozin: In adult patients with type 2 diabetes mellitus with mild (eGFR: 60 to less than 90 mL/min/1.73 m^2), moderate (eGFR: 30 to less than 60 mL/min/1.73 m^2), and severe (eGFR: less than 30 mL/min/1.73 m^2) renal impairment and patients on dialysis due to kidney failure, AUC of empagliflozin increased by approximately 18%, 20%, 66%, and 48%, respectively, compared to subjects with normal renal function. Peak plasma levels of empagliflozin were similar in patients with moderate renal impairment and patients on dialysis due to kidney failure, compared to subjects with normal renal function. Peak plasma levels of empagliflozin were roughly 20% higher in patients with mild and severe renal impairment as compared to patients with normal renal function. Population pharmacokinetic analysis showed that the apparent oral clearance of empagliflozin decreased with a decrease in eGFR leading to an increase in drug exposure. However, the fraction of empagliflozin that was excreted unchanged in urine, and urinary glucose excretion, declined with decrease in eGFR.

Metformin HCl: In patients with decreased renal function, the plasma and blood half-life of metformin is prolonged and the renal clearance is decreased [see Contraindications (4) and Warnings and Precautions (5.1)].

Patients with Hepatic Impairment

SYNJARDY or SYNJARDY XR: Studies characterizing the pharmacokinetics of empagliflozin and metformin after administration of SYNJARDY or SYNJARDY XR in hepatically impaired patients have not been performed [see Warnings and Precautions (5.1)].

Empagliflozin: In adult patients with mild, moderate, and severe hepatic impairment according to the Child-Pugh classification, AUC of empagliflozin increased by approximately 23%, 47%, and 75%, and Cmax increased by approximately 4%, 23%, and 48%, respectively, compared to subjects with normal hepatic function.

Metformin HCl: No pharmacokinetic studies of metformin have been conducted in patients with hepatic impairment.

Drug Interaction Studies

Pharmacokinetic drug interaction studies with SYNJARDY or SYNJARDY XR have not been performed; however, such studies have been conducted with the individual components empagliflozin and metformin HCl.

Empagliflozin

In vitro Assessment of Drug Interactions: Empagliflozin does not inhibit, inactivate, or induce CYP450 isoforms. In vitro data suggest that the primary route of metabolism of empagliflozin in humans is glucuronidation by the uridine 5'-diphospho-glucuronosyltransferases UGT1A3, UGT1A8, UGT1A9, and UGT2B7. Empagliflozin does not inhibit UGT1A1, UGT1A3, UGT1A8, UGT1A9, or UGT2B7. Therefore, no effect of empagliflozin is anticipated on concomitantly administered drugs that are substrates of the major CYP450 isoforms or UGT1A1, UGT1A3, UGT1A8, UGT1A9, or UGT2B7. The effect of UGT induction (e.g., induction by rifampicin or any other UGT enzyme inducer) on empagliflozin exposure has not been evaluated.

Empagliflozin is a substrate for P-glycoprotein (P-gp) and breast cancer resistance protein (BCRP), but it does not inhibit these efflux transporters at therapeutic doses. Based on in vitro studies, empagliflozin is considered unlikely to cause interactions with drugs that are P-gp substrates. Empagliflozin is a substrate of the human uptake transporters OAT3, OATP1B1, and OATP1B3, but not OAT1 and OCT2. Empagliflozin does not inhibit any of these human uptake transporters at clinically relevant plasma concentrations and, therefore, no effect of empagliflozin is anticipated on concomitantly administered drugs that are substrates of these uptake transporters.

In vivo Assessment of Drug Interactions: Empagliflozin pharmacokinetics were similar with and without coadministration of metformin HCl, glimepiride, pioglitazone, sitagliptin, linagliptin, warfarin, verapamil, ramipril, and simvastatin in healthy volunteers and with or without coadministration of hydrochlorothiazide and torsemide in patients with type 2 diabetes mellitus (see Figure 1). In subjects with normal renal function, coadministration of empagliflozin with probenecid resulted in a 30% decrease in the fraction of empagliflozin excreted in urine without any effect on 24-hour urinary glucose excretion. The relevance of this observation to patients with renal impairment is unknown.

Figure 1 Effect of Various Medications on the Pharmacokinetics of Empagliflozin as Displayed as 90% Confidence Interval of Geometric Mean AUC and Cmax Ratios [reference lines indicate 100% (80% - 125%)]

aempagliflozin, 50 mg, once daily; bempagliflozin, 25 mg, single dose; cempagliflozin, 25 mg, once daily; dempagliflozin, 10 mg, single dose

Empagliflozin had no clinically relevant effect on the pharmacokinetics of metformin, glimepiride, pioglitazone, sitagliptin, linagliptin, warfarin, digoxin, ramipril, simvastatin, hydrochlorothiazide, torsemide, and oral contraceptives when coadministered in healthy volunteers (see Figure 2).

Figure 2 Effect of Empagliflozin on the Pharmacokinetics of Various Medications as Displayed as 90% Confidence Interval of Geometric Mean AUC and Cmax Ratios [reference lines indicate 100% (80% - 125%)]

aempagliflozin, 50 mg, once daily; bempagliflozin, 25 mg, once daily; cempagliflozin, 25 mg, single dose; dadministered as simvastatin; eadministered as warfarin racemic mixture; fadministered as Microgynon®; gadministered as ramipril

Metformin HCl

Table 5 Effect of Coadministered Drug on Plasma Metformin Systemic Exposure
Coadministered Drug | Dose of Coadministered Drug* | Dose of Metformin HCl* | Geometric Mean Ratio (ratio with/without coadministered drug) No effect=1.0
Coadministered Drug | Dose of Coadministered Drug* | Dose of Metformin HCl* |  | AUC† | Cmax
Glyburide | 5 mg | 500 mg≠ | metformin | 0.98‡ | 0.99‡
Furosemide | 40 mg | 850 mg | metformin | 1.09‡ | 1.22‡
Nifedipine | 10 mg | 850 mg | metformin | 1.16 | 1.21
Propranolol | 40 mg | 850 mg | metformin | 0.90 | 0.94
Ibuprofen | 400 mg | 850 mg | metformin | 1.05‡ | 1.07‡
Cationic drugs eliminated by renal tubular secretion may reduce metformin elimination [see Drug Interactions (7)].
Cimetidine | 400 mg | 850 mg | metformin | 1.40 | 1.61
Carbonic anhydrase inhibitors may cause metabolic acidosis [see Drug Interactions (7)].
Topiramate** | 100 mg | 500 mg | metformin | 1.25 | 1.17
* All metformin and coadministered drugs were given as single doses
† AUC = AUC (INF)
≠ Metformin HCl extended-release tablets 500 mg
‡ Ratio of arithmetic means
**At steady-state with topiramate 100 mg every 12 hours and metformin 500 mg every 12 hours; AUC = AUC (0-12 hours)

Table 6 Effect of Metformin on Coadministered Drug Systemic Exposure
Coadministered Drug | Dose of Coadministered Drug* | Dose of Metformin HCl* | Geometric Mean Ratio (ratio with/without metformin) No effect=1.0
Coadministered Drug | Dose of Coadministered Drug* | Dose of Metformin HCl* |  | AUC† | Cmax
Glyburide | 5 mg | 500 mg§ | glyburide | 0.78‡ | 0.63‡
Furosemide | 40 mg | 850 mg | furosemide | 0.87‡ | 0.69‡
Nifedipine | 10 mg | 850 mg | nifedipine | 1.10§ | 1.08
Propranolol | 40 mg | 850 mg | propranolol | 1.01§ | 0.94
Ibuprofen | 400 mg | 850 mg | ibuprofen | 0.97¶ | 1.01¶
Cimetidine | 400 mg | 850 mg | cimetidine | 0.95§ | 1.01
* All metformin and coadministered drugs were given as single doses
† AUC = AUC (INF) unless otherwise noted
‡ Ratio of arithmetic means, p-value of difference <0.05
§ AUC (0-24 hours) reported
¶ Ratio of arithmetic means

13 NONCLINICAL TOXICOLOGY

13.1 Carcinogenesis, Mutagenesis, Impairment of Fertility

SYNJARDY or SYNJARDY XR

No carcinogenicity, mutagenicity, or impairment of fertility studies have been conducted with the combination of empagliflozin and metformin HCl. General toxicity studies in rats up to 13 weeks were performed with the combined components. These studies indicated that no additive toxicity is caused by the combination of empagliflozin and metformin HCl.

Empagliflozin

Carcinogenesis was evaluated in 2-year studies conducted in CD-1 mice and Wistar rats. Empagliflozin did not increase the incidence of tumors in female rats dosed at 100, 300, or 700 mg/kg/day (up to 72 times the exposure from the maximum clinical dose of 25 mg). In male rats, hemangiomas of the mesenteric lymph node were increased significantly at 700 mg/kg/day or approximately 42 times the exposure from a 25 mg clinical dose. Empagliflozin did not increase the incidence of tumors in female mice dosed at 100, 300, or 1,000 mg/kg/day (up to 62 times the exposure from a 25 mg clinical dose). Renal tubule adenomas and carcinomas were observed in male mice at 1,000 mg/kg/day, which is approximately 45 times the exposure of the maximum clinical dose of 25 mg. These tumors may be associated with a metabolic pathway predominantly present in the male mouse kidney.

Empagliflozin was not mutagenic or clastogenic with or without metabolic activation in the in vitro Ames bacterial mutagenicity assay, the in vitro L5178Y tk+/- mouse lymphoma cell assay, and an in vivo micronucleus assay in rats.

Empagliflozin had no effects on mating, fertility or early embryonic development in treated male or female rats up to the high dose of 700 mg/kg/day (approximately 155 times the 25 mg clinical dose in males and females, respectively).

Metformin HCl

Long-term carcinogenicity studies have been performed in rats (dosing duration of 104 weeks) and mice (dosing duration of 91 weeks) at doses up to and including 900 mg/kg/day and 1,500 mg/kg/day, respectively. These doses are both approximately 4 times the maximum recommended human daily dose of 2,000 mg/kg/day based on body surface area comparisons. No evidence of carcinogenicity with metformin was found in either male or female mice. Similarly, there was no tumorigenic potential observed with metformin in male rats. There was, however, an increased incidence of benign stromal uterine polyps in female rats treated with 900 mg/kg/day.

There was no evidence of a mutagenic potential of metformin in the following in vitro tests: Ames test (Salmonella typhimurium), gene mutation test (mouse lymphoma cells), or chromosomal aberrations test (human lymphocytes). Results in the in vivo mouse micronucleus test were also negative.

Fertility of male or female rats was unaffected by metformin when administered at doses as high as 600 mg/kg/day, which is approximately 2 times the MRHD based on body surface area comparisons.

14 CLINICAL STUDIES

14.1 Glycemic Control Trials in Adults with Type 2 Diabetes Mellitus

In adult patients with type 2 diabetes mellitus, treatment with empagliflozin and metformin HCl produced clinically and statistically significant improvements in HbA1c compared to placebo and metformin HCl. Reductions in HbA1c were observed across subgroups including age, sex, race, and baseline BMI.

Empagliflozin Add-On Combination Therapy with Metformin HCl in Adult Patients with Type 2 Diabetes Mellitus

A total of 637 patients with type 2 diabetes mellitus participated in a double-blind, placebo-controlled trial to evaluate the efficacy of empagliflozin in combination with metformin HCl.

Patients with type 2 diabetes mellitus inadequately controlled on at least 1,500 mg of metformin HCl per day entered an open-label 2-week placebo run-in. At the end of the run-in period, patients who remained inadequately controlled and had an HbA1c between 7% and 10% were randomized to placebo, empagliflozin 10 mg, or empagliflozin 25 mg.

At Week 24, treatment with empagliflozin 10 mg or 25 mg daily provided statistically significant reductions in HbA1c (p-value <0.0001), FPG, and body weight compared with placebo (see Table 7).

Table 7 Results at Week 24 From a Placebo-Controlled Trial for Empagliflozin used in Combination with Metformin HCl
 | Empagliflozin 10 mg N=217 | Empagliflozin 25 mg N=213 | Placebo N=207
HbA1c (%)a
Baseline (mean) | 7.9 | 7.9 | 7.9
Change from baseline (adjusted mean) | -0.7 | -0.8 | -0.1
Difference from placebo + metformin HCl (adjusted mean) (95% CI) | -0.6b (-0.7, -0.4) | -0.6b (-0.8, -0.5) | --
Patients [n (%)] achieving HbA1c <7% | 75 (38%) | 74 (39%) | 23 (13%)
FPG (mg/dL)c
Baseline (mean) | 155 | 149 | 156
Change from baseline (adjusted mean) | -20 | -22 | 6
Difference from placebo + metformin HCl (adjusted mean) | -26 | -29 | --
Body Weight
Baseline mean in kg | 82 | 82 | 80
% change from baseline (adjusted mean) | -2.5 | -2.9 | -0.5
Difference from placebo (adjusted mean) (95% CI) | -2.0b (-2.6, -1.4) | -2.5b (-3.1, -1.9) | --
aModified intent-to-treat population. Last observation on trial (LOCF) was used to impute missing data at Week 24. At Week 24, 9.7%, 14.1%, and 24.6% was imputed for patients randomized to empagliflozin 10 mg, empagliflozin 25 mg, and placebo, respectively.
bANCOVA p-value <0.0001 (HbA1c: ANCOVA model includes baseline HbA1c, treatment, renal function, and region. Body weight and FPG: same model used as for HbA1c but additionally including baseline body weight/baseline FPG, respectively.)
cFPG (mg/dL); for empagliflozin 10 mg, n=216, for empagliflozin 25 mg, n=213, and for placebo, n=207

At Week 24, the systolic blood pressure was statistically significantly reduced compared to placebo by -4.1 mmHg (placebo-corrected, p-value <0.0001) for empagliflozin 10 mg and -4.8 mmHg (placebo-corrected, p-value <0.0001) for empagliflozin 25 mg.

Empagliflozin Initial Combination Therapy with Metformin HCl

A total of 1,364 patients with type 2 diabetes mellitus participated in a double-blind, randomized, active-controlled trial to evaluate the efficacy of empagliflozin in combination with metformin HCl as initial therapy compared to the corresponding individual components.

Treatment-naïve patients with inadequately controlled type 2 diabetes mellitus entered an open-label placebo run-in for 2 weeks. At the end of the run-in period, patients who remained inadequately controlled and had an HbA1c between 7% and 10.5% were randomized to one of 8 active-treatment arms: empagliflozin 10 mg or 25 mg; metformin HCl 1,000 mg, or 2,000 mg; empagliflozin 10 mg in combination with 1,000 mg or 2,000 mg metformin HCl; or empagliflozin 25 mg in combination with 1,000 mg or 2,000 mg metformin HCl.

At Week 24, initial therapy of empagliflozin in combination with metformin HCl provided statistically significant reductions in HbA1c (p-value <0.01) compared to the individual components (see Table 8).

Table 8 Glycemic Parameters at 24 Weeks in a Trial Comparing Empagliflozin and Metformin HCl to the Individual Components as Initial Therapy
 | Empagliflozin 10 mg + Metformin HCl 1,000 mga N=161 | Empagliflozin 10 mg + Metformin HCl 2,000 mga N=167 | Empagliflozin 25 mg + Metformin HCl 1,000 mga N=165 | Empagliflozin 25 mg + Metformin HCl 2,000 mga N=169 | Empagliflozin 10 mg N=169 | Empagliflozin 25 mg N=163 | Metformin HCl 1,000 mga N=167 | Metformin HCl 2,000 mga N=162
HbA1c (%)
Baseline (mean) | 8.7 | 8.7 | 8.8 | 8.7 | 8.6 | 8.9 | 8.7 | 8.6
Change from baseline (adjusted mean) | -2.0 | -2.1 | -1.9 | -2.1 | -1.4 | -1.4 | -1.2 | -1.8
Comparison vs empagliflozin (adjusted mean) (95% CI) | -0.6b (-0.9, -0.4) | -0.7b (-1.0, -0.5) | -0.6c (-0.8, -0.3) | -0.7c (-1.0, -0.5) | -- | -- | -- | --
Comparison vs metformin HCl (adjusted mean) (95% CI) | -0.8b (-1.0, -0.6) | -0.3b (-0.6, -0.1) | -0.8c (-1.0, -0.5) | -0.3c (-0.6, -0.1) | -- | -- | -- | --
Patients [n (%)] achieving HbA1c <7% | 96 (63%) | 112 (70%) | 91 (57%) | 111 (68%) | 69 (43%) | 51 (32%) | 63 (38%) | 92 (58%)
aMetformin HCl total daily dose, administered in two equally divided doses per day.
bp-value ≤0.0062 (modified intent-to-treat population [observed case] MMRM model included treatment, renal function, region, visit, visit by treatment interaction, and baseline HbA1c).
cp-value ≤0.0056 (modified intent-to-treat population [observed case] MMRM model included treatment, renal function, region, visit, visit by treatment interaction, and baseline HbA1c).

Empagliflozin Add-On Combination Therapy with Metformin HCl and Sulfonylurea

A total of 666 patients with type 2 diabetes mellitus participated in a double-blind, placebo-controlled trial to evaluate the efficacy of empagliflozin in combination with metformin HCl plus a sulfonylurea.

Patients with inadequately controlled type 2 diabetes mellitus on at least 1,500 mg per day of metformin HCl and on a sulfonylurea, entered a 2-week open-label placebo run-in. At the end of the run-in, patients who remained inadequately controlled and had an HbA1c between 7% and 10% were randomized to placebo, empagliflozin 10 mg, or empagliflozin 25 mg.

Treatment with empagliflozin 10 mg or 25 mg daily provided statistically significant reductions in HbA1c (p-value <0.0001), FPG, and body weight compared with placebo (see Table 9).

Table 9 Results at Week 24 from a Placebo-Controlled Trial for Empagliflozin in Combination with Metformin HCl and Sulfonylurea
 | Empagliflozin 10 mg N=225 | Empagliflozin 25 mg N=216 | Placebo N=225
HbA1c (%)a
Baseline (mean) | 8.1 | 8.1 | 8.2
Change from baseline (adjusted mean) | -0.8 | -0.8 | -0.2
Difference from placebo (adjusted mean) (95% CI) | -0.6b (-0.8, -0.5) | -0.6b (-0.7, -0.4) | --
Patients [n (%)] achieving HbA1c <7% | 55 (26%) | 65 (32%) | 20 (9%)
FPG (mg/dL)c
Baseline (mean) | 151 | 156 | 152
Change from baseline (adjusted mean) | -23 | -23 | 6
Difference from placebo (adjusted mean) | -29 | -29 | --
Body Weight
Baseline mean in kg | 77 | 78 | 76
% change from baseline (adjusted mean) | -2.9 | -3.2 | -0.5
Difference from placebo (adjusted mean) (95% CI) | -2.4b (-3.0, -1.8) | -2.7b (-3.3, -2.1) | --
aModified intent-to-treat population. Last observation on trial (LOCF) was used to impute missing data at Week 24. At Week 24, 17.8%, 16.7%, and 25.3% was imputed for patients randomized to empagliflozin 10 mg, empagliflozin 25 mg, and placebo, respectively.
bANCOVA p-value <0.0001 (HbA1c: ANCOVA model includes baseline HbA1c, treatment, renal function, and region. Body weight and FPG: same model used as for HbA1c but additionally including baseline body weight/baseline FPG, respectively.)
cFPG (mg/dL); for empagliflozin 10 mg, n=225, for empagliflozin 25 mg, n=215, for placebo, n=224

Active-Controlled Trial vs Glimepiride in Combination with Metformin HCl

The efficacy of empagliflozin was evaluated in a double-blind, glimepiride-controlled, trial in 1,545 patients with type 2 diabetes mellitus with insufficient glycemic control despite metformin HCl therapy.

Patients with inadequate glycemic control and an HbA1c between 7% and 10% after a 2-week run-in period were randomized to glimepiride or empagliflozin 25 mg.

At Week 52, empagliflozin 25 mg and glimepiride lowered HbA1c and FPG (see Table 10, Figure 3). The difference in observed effect size between empagliflozin 25 mg and glimepiride excluded the pre-specified non-inferiority margin of 0.3%. The mean daily dosage of glimepiride was 2.7 mg and the maximal approved dosage in the United States is 8 mg per day.

Table 10 Results at Week 52 from an Active-Controlled Trial Comparing Empagliflozin to Glimepiride as Add-On Therapy in Patients Inadequately Controlled on Metformin HCl
 | Empagliflozin 25 mg N=765 | Glimepiride N=780
HbA1c (%)a
Baseline (mean) | 7.9 | 7.9
Change from baseline (adjusted mean) | -0.7 | -0.7
Difference from glimepiride (adjusted mean) (97.5% CI) | -0.07b (-0.15, 0.01) | --
FPG (mg/dL)d
Baseline (mean) | 150 | 150
Change from baseline (adjusted mean) | -19 | -9
Difference from glimepiride (adjusted mean) | -11 | --
Body Weight
Baseline mean in kg | 82.5 | 83
% change from baseline (adjusted mean) | -3.9 | 2.0
Difference from glimepiride (adjusted mean) (95% CI) | -5.9c (-6.3, -5.5) | --
aModified intent-to-treat population. Last observation on trial (LOCF) was used to impute data missing at Week 52. At Week 52, data was imputed for 15.3% and 21.9% of patients randomized to empagliflozin 25 mg and glimepiride, respectively.
bNon-inferior, ANCOVA model p-value <0.0001 (HbA1c: ANCOVA model includes baseline HbA1c, treatment, renal function, and region)
cANCOVA p-value <0.0001 (Body weight and FPG: same model used as for HbA1c but additionally including baseline body weight/baseline FPG, respectively.)
dFPG (mg/dL); for empagliflozin 25 mg, n=764, for glimepiride, n=779

Figure 3 Adjusted mean HbA1c Change at Each Time Point (Completers) and at Week 52 (mITT Population) – LOCF

At Week 52, the adjusted mean change from baseline in systolic blood pressure was -3.6 mmHg, compared to 2.2 mmHg for glimepiride. The differences between treatment groups for systolic blood pressure was statistically significant (p-value <0.0001).

At Week 104, the adjusted mean change from baseline in HbA1c was -0.75% for empagliflozin 25 mg and -0.66% for glimepiride. The adjusted mean treatment difference was -0.09% with a 97.5% confidence interval of (-0.32%, 0.15%), excluding the pre-specified non-inferiority margin of 0.3%. The mean daily dosage of glimepiride was 2.7 mg and the maximal approved dosage in the United States is 8 mg per day. The Week 104 analysis included data with and without concomitant glycemic rescue medication, as well as off-treatment data. Missing data for patients not providing any information at the visit were imputed based on the observed off-treatment data. In this multiple imputation analysis, 13.9% of the data were imputed for empagliflozin 25 mg and 12.9% for glimepiride.

At Week 104, empagliflozin 25 mg daily resulted in a statistically significant difference in change from baseline for body weight compared to glimepiride (-3.1 kg for empagliflozin 25 mg vs. +1.3 kg for glimepiride; ANCOVA-LOCF, p-value <0.0001).

14.2 Glycemic Control Trials in Pediatric Patients with Type 2 Diabetes Mellitus

Glycemic Control Trial of Empagliflozin in Pediatric Patients Aged 10 to 17 Years with Type 2 Diabetes Mellitus

DINAMO (NCT03429543) was a 26-week, double-blind, randomized, placebo-controlled, parallel group trial, with a double-blind active treatment safety extension period up to 52 weeks to assess the efficacy of empagliflozin. The trial enrolled pediatric patients aged 10 to 17 years with inadequately controlled type 2 diabetes mellitus (HbA1c 6.5 to 10.5%). Patients treated with metformin HCl (at least 1,000 mg daily or maximally tolerated dose), with or without insulin therapy, and those with a history of intolerance to metformin HCl therapy were enrolled. Patients were randomized to 3 treatment arms (empagliflozin 10 mg, a dipeptidyl peptidase-4 (DPP-4) inhibitor, or placebo) over 26 weeks. Patients in the empagliflozin 10 mg group who failed to achieve HbA1c <7.0% at Week 12 underwent a second randomization at Week 14 to remain on the 10 mg dose or increase to 25 mg. Patients on placebo were re-randomized at Week 26 to one of the empagliflozin doses (10 mg or 25 mg) or a DPP-4 inhibitor.

A total of 157 patients were treated with either empagliflozin (10 mg or 25 mg; N=52), a DPP-4 inhibitor (N=52), or placebo (N=53). Background therapies as adjunct to diet and exercise included metformin HCl (51%), a combination of metformin HCl and insulin (40.1%), insulin (3.2%), or none (5.7%). The mean HbA1c at baseline was 8.0% and the mean duration of type 2 diabetes mellitus was 2.1 years. The mean age was 14.5 years (range: 10-17 years) and 51.6% were aged 15 years and older. Approximately, 50% were White, 6% were Asian, 31% were Black or African American, and 38% were of Hispanic or Latino ethnicity. The mean BMI was 36.0 kg/m^2 and mean BMI Z-score was 3.0. Patients with an eGFR less than 60 mL/min/1.73 m^2 were not enrolled in the trial. Approximately 25% of the trial population had microalbuminuria or macroalbuminuria.

At Week 26, treatment with empagliflozin was superior in reducing HbA1c from baseline versus placebo (see Table 11).

Table 11 Results at Week 26 for a Placebo-Controlled Trial for Empagliflozin in Combination with Metformin HCl and/or Insulin or as Monotherapy in Pediatric Patients Aged 10 to 17 Years with Type 2 Diabetes Mellitusa
 | Empagliflozin 10 mg and 25 mg | Placebo
HbA1c (%)b
Number of patients | n=52 | n=53
Baseline (mean) | 8.0 | 8.1
Change from baselinec | -0.2 | 0.7
Difference from placeboc (95% CI) | -0.8e (-1.5, -0.2) | --
FPG (mg/dL)b,d
Number of patients | n=48 | n=52
Baseline (mean) | 154 | 159
Change from baselinec | -19 | 17
Difference from placeboc (95% CI) | -36 (-60.7, -10.7) | --
aModified intent-to-treat set (All randomized and treated patients with baseline measurement).
bMultiple imputations using placebo wash-out approach with 500 iterations for missing data. Imputed for HbA1c (empagliflozin N=5 (9.6%), placebo N=3 (5.7%)), for FPG (empagliflozin N=4 (8.3%), placebo N=2 (3.8%)).
cLeast-Square Mean from Analysis of Covariance (ANCOVA) adjusted for baseline value and baseline age stratum (< 15 years vs 15 to < 18 years).
dNot evaluated for statistical significance, not part of sequential testing procedure.
ep-value=0.0116 (two-sided)

Glycemic Control Trial of Metformin HCl Immediate-Release in Pediatric Patients Aged 10 to 16 Years with Type 2 Diabetes Mellitus:

A double-blind, placebo-controlled trial was conducted in pediatric patients aged 10 to 16 years with type 2 diabetes mellitus (mean FPG 182.2 mg/dL), where patients were treated with metformin HCl immediate-release tablets (up to 2,000 mg/day) for up to 16 weeks (mean duration of treatment 11 weeks). The results are displayed in Table 12.

Table 12 Mean Change in Fasting Plasma Glucose at Week 16 Comparing Metformin HCl vs. Placebo in Pediatric Patientsa with Type 2 Diabetes Mellitus
 | Metformin HCl | Placebo | p-value
FPG (mg/dL) | (n=37) | (n=36)
Baseline | 162.4 | 192.3
Change at FINAL VISIT | -42.9 | 21.4 | <0.001
a Pediatric patients mean age 13.8 years (range 10-16 years)

Mean baseline body weight was 205 lbs and 189 lbs in the metformin HCl immediate-release and placebo arms, respectively. Mean change in body weight from baseline to week 16 was -3.3 lbs and -2.0 lbs in the metformin HCl and placebo arms, respectively.

14.3 Empagliflozin CV Outcome Trial in Adult Patients with Type 2 Diabetes Mellitus and Atherosclerotic CV Disease

EMPA-REG OUTCOME was a multicenter, multinational, randomized, double-blind parallel group trial that compared the risk of experiencing a major adverse CV event (MACE) between empagliflozin and placebo when these were added to and used concomitantly with standard of care treatments for diabetes mellitus and atherosclerotic CV disease. Concomitant antidiabetic medications were kept stable for the first 12 weeks of the trial. Thereafter, antidiabetic and atherosclerotic therapies could be adjusted, at the discretion of investigators, to ensure participants were treated according to the standard care for these diseases.

A total of 7,020 patients were treated (empagliflozin 10 mg = 2,345; empagliflozin 25 mg = 2,342; placebo = 2,333) and followed for a median of 3.1 years. Approximately 72% of the trial population was White, 22% was Asian, and 5% was Black or African American. The mean age was 63 years and approximately 72% were male.

All patients in the trial had inadequately controlled type 2 diabetes mellitus at baseline (HbA1c greater than or equal to 7%). The mean HbA1c at baseline was 8.1% and 57% of participants had diabetes mellitus for more than 10 years. Approximately 31%, 22% and 20% reported a past history of neuropathy, retinopathy and nephropathy to investigators, respectively and the mean eGFR was 74 mL/min/1.73 m^2. At baseline, patients were treated with one (~30%) or more (~70%) antidiabetic medications including metformin HCl (74%), insulin (48%), and sulfonylurea (43%).

All patients had established atherosclerotic CV disease at baseline including one (82%) or more (18%) of the following: a documented history of coronary artery disease (76%), stroke (23%) or peripheral artery disease (21%). At baseline, the mean systolic blood pressure was 136 mmHg, the mean diastolic blood pressure was 76 mmHg, the mean LDL was 86 mg/dL, the mean HDL was 44 mg/dL, and the mean urinary albumin to creatinine ratio (UACR) was 175 mg/g. At baseline, approximately 81% of patients were treated with renin angiotensin system inhibitors, 65% with beta-blockers, 43% with diuretics, 77% with statins, and 86% with antiplatelet agents (mostly aspirin).

The primary endpoint in EMPA-REG OUTCOME was the time to first occurrence of a Major Adverse Cardiac Event (MACE). A major adverse cardiac event was defined as occurrence of either a CV death or a non-fatal myocardial infarction (MI) or a non-fatal stroke. The statistical analysis plan had pre-specified that the 10 and 25 mg dosages would be combined. A Cox proportional hazards model was used to test for non-inferiority against the pre-specified risk margin of 1.3 for the hazard ratio of MACE and superiority on MACE if non-inferiority was demonstrated. Type-1 error was controlled across multiples tests using a hierarchical testing strategy.

Empagliflozin significantly reduced the risk of first occurrence of primary composite endpoint of CV death, non-fatal myocardial infarction, or non-fatal stroke (HR: 0.86; 95% CI: 0.74, 0.99). The treatment effect was due to a significant reduction in the risk of CV death in subjects randomized to empagliflozin (HR: 0.62; 95% CI: 0.49, 0.77), with no change in the risk of non-fatal myocardial infarction or non-fatal stroke (see Table 13 and Figures 4 and 5). Results for the 10 mg and 25 mg empagliflozin dosages were consistent with results for the combined dosage groups.

Table 13 Treatment Effect for the Primary Composite Endpoint and its Componentsa
 | Placebo N=2,333 | Empagliflozin N=4,687 | Hazard ratio vs placebo (95% CI)
Composite of CV death, non-fatal myocardial infarction, non-fatal stroke (time to first occurrence)b | 282 (12.1%) | 490 (10.5%) | 0.86 (0.74, 0.99)
Non-fatal myocardial infarctionc | 121 (5.2%) | 213 (4.5%) | 0.87 (0.70, 1.09)
Non-fatal strokec | 60 (2.6%) | 150 (3.2%) | 1.24 (0.92, 1.67)
CV deathc | 137 (5.9%) | 172 (3.7%) | 0.62 (0.49, 0.77)
aTreated set (patients who had received at least one dose of trial drug)
bp-value for superiority (2-sided) 0.04
cTotal number of events

Figure 4 Estimated Cumulative Incidence of First MACE

Figure 5 Estimated Cumulative Incidence of CV Death

The efficacy of empagliflozin on CV death was generally consistent across major demographic and disease subgroups.

Vital status was obtained for 99.2% of subjects in the trial. A total of 463 deaths were recorded during the EMPA-REG OUTCOME trial. Most of these deaths were categorized as CV deaths. The non-CV deaths were only a small proportion of deaths and were balanced between the treatment groups (2.1% in patients treated with empagliflozin, and 2.4% of patients treated with placebo).

14.4 Empagliflozin Heart Failure Trials, Including Adult Patients with Type 2 Diabetes Mellitus

EMPEROR-Reduced Trial (Chronic Heart Failure with Left Ventricular Ejection Fraction ≤ 40%)

EMPEROR-Reduced (NCT03057977) was a double-blind trial conducted in adults with chronic heart failure [New York Heart Association (NYHA) functional class II-IV] with left ventricular ejection fraction (LVEF) ≤40% to evaluate the efficacy of empagliflozin as adjunct to standard of care heart failure therapy. Of 3,730 patients, 1,863 were randomized to empagliflozin 10 mg once daily and 1,867 to placebo once daily and were followed for a median of 16 months.

Baseline Disease Characteristics and Demographics

EMPEROR-Reduced included patients with type 2 diabetes mellitus (n=1,856) and patients without type 2 diabetes mellitus (n=1,874). The mean age of the trial population was 67 years (range: 25 to 94 years) and 76% were males, 24% were women, and 27% were 75 years of age or older. Approximately 71% of the trial population were White, 18% Asian and 7% Black or African American. At randomization, 75% of patients were NYHA class II, 24% were class III and 0.5% were class IV. The mean LVEF was 28%. At baseline, the mean eGFR was 62 mL/min/1.73 m^2 and the median urinary albumin to creatinine ratio (UACR) was 22 mg/g. Approximately half of the patients (52%) had eGFR equal to or above 60 mL/min/1.73 m^2, 24% had eGFR 45 to less than 60 mL/min/1.73 m^2, and 19% had eGFR 30 to less than 45 mL/min/1.73 m^2. At baseline, 88% of patients were treated with angiotensin-converting enzyme (ACE) inhibitors, angiotensin receptor blockers (ARB), or angiotensin receptor-neprilysin inhibitors (ARNI), 95% with beta-blockers, 71% with mineralocorticoid receptor antagonists (MRA), and 95% with diuretics.

In EMPEROR-Reduced, history of type 2 diabetes mellitus was present in 50% of the patients, and 46% of these patients were treated with metformin HCl (444 patients in the empagliflozin group and 418 in the placebo group) and 25% were treated with insulin. In the type 2 diabetes mellitus subpopulation, the mean age was 67 years; 77% were males; 69% White, 19% Asian and 7% Black or African American; 32% were Hispanic/Latino. In the type 2 diabetes mellitus subpopulation, at baseline, 71% of patients were classified as NYHA class II, 28% class III and 0.7% class IV; the mean LVEF was 27%; the mean baseline eGFR was 61 mL/min/1.73 m^2. In this subpopulation, at baseline, 88% of patients were treated with ACE inhibitors, ARB, or ARNI, 95% with beta-blockers, 70% with MRA, and 96% with diuretics.

Results

In EMPEROR-Reduced, empagliflozin 10 mg, compared with placebo, reduced the risk of the primary composite endpoint of CV death or hospitalization for heart failure (HHF) mostly through a reduction in HHF (HR 0.75 [95% CI 0.65, 0.86]). Empagliflozin reduced the risk of first and recurrent HHF, a key secondary endpoint. Because of the metformin HCl component, SYNJARDY and SYNJARDY XR are not indicated for use in patients with heart failure without type 2 diabetes mellitus [see Indications and Usage (1)].

The effect of empagliflozin in reducing the risk of the primary composite endpoint was consistent in patients with type 2 diabetes mellitus (HR 0.73 [95% CI 0.60, 0.87]), and in patients with type 2 diabetes mellitus and metformin HCl as background therapy (HR 0.65 [95% CI 0.49, 0.86]).

EMPEROR-Preserved Trial (Chronic Heart Failure with Left Ventricular Ejection Fraction > 40%)

EMPEROR-Preserved (NCT03057951) was a double-blind trial conducted in patients with chronic heart failure NYHA Class II-IV with LVEF >40% to evaluate the efficacy of empagliflozin as adjunct to standard of care therapy. Of 5,988 patients, 2,997 patients were randomized to empagliflozin 10 mg once daily and 2,991 patients to placebo once daily and were followed for a median of 26 months.

Baseline Disease Characteristics and Demographics

EMPEROR-Preserved included patients with type 2 diabetes mellitus (n=2,928) and patients without type 2 diabetes mellitus (n=3,060). The mean age of the trial population was 72 years (range: 22 to 100 years) and 55% were males, 45% were women, and 43% were 75 years of age or older. Approximately 76% of the trial population were White, 14% Asian and 4% Black or African American. At randomization, 82% of patients were NYHA class II, 18% were class III and 0.3% were class IV. This trial included patients with a LVEF <50% (33.1%), with a LVEF 50 to <60% (34.4%) and a LVEF ≥60% (32.5%). At baseline, the mean eGFR was 61 mL/min/1.73 m^2 and the median urinary albumin to creatinine ratio (UACR) was 21 mg/g. Approximately half of the patients (50%) had eGFR equal to or above 60 mL/min/1.73 m^2, 26% had eGFR 45 to less than 60 mL/min/1.73 m^2, and 19% had eGFR 30 to less than 45 mL/min/1.73 m^2. At baseline, 81% of patients were treated with ACE inhibitors, ARBs, or ARNI, 86% with beta-blockers, 38% with MRAs, and 86% with diuretics.

In EMPEROR-Preserved, history of type 2 diabetes mellitus was present in 49% of the patients, and 54% of these patients were treated with metformin HCl (773 patients in the empagliflozin group and 803 in the placebo group) and 29% were treated with insulin. In the type 2 diabetes mellitus subpopulation, the mean age was 71 years, 57% were males, 75% White, 13% Asian and 5% Black or African American. In the type 2 diabetes mellitus subpopulation, at baseline, 79% of patients were classified as NYHA class II, 20% class III and 0.2% class IV; the trial also included type 2 diabetics with LVEF <50% (35%), with a LVEF 50 to <60% (34%) and a LVEF ≥60% (31%). For this subpopulation, the mean baseline eGFR was 60 mL/min/1.73 m^2; and at baseline, 83% of patients were treated with ACE inhibitors, ARB, or ARNI, 88% with beta-blockers, 39% with MRA, and 89% with diuretics.

Results

In EMPEROR-Preserved, empagliflozin 10 mg, compared with placebo, reduced the risk of the primary composite endpoint (time to first event of either CV death or HHF) mostly through a reduction in hospitalization for heart failure (HR 0.79 [95% CI 0.69, 0.90]). Empagliflozin reduced the risk of first and recurrent HHF, a key secondary endpoint. Because of the metformin HCl component, SYNJARDY and SYNJARDY XR are not indicated for use in patients with heart failure without type 2 diabetes mellitus [see Indications and Usage (1)].

The effect of empagliflozin in reducing the risk of the primary composite endpoint was consistent in patients with type 2 diabetes mellitus (HR 0.80 [95% CI 0.67, 0.95]), and in patients with type 2 diabetes mellitus and metformin HCl as background therapy (HR 0.79 [95% CI 0.61, 1.02]).

14.5 Empagliflozin Chronic Kidney Disease Trial, Including Adult Patients with Type 2 Diabetes Mellitus

The effectiveness of empagliflozin, a component of SYNJARDY and SYNJARDY XR, to reduce the risk of sustained decline in eGFR, end-stage kidney disease, CV death, and hospitalization has been established in adults with chronic kidney disease at risk of progression based on an adequate and well-controlled study of empagliflozin [EMPA-KIDNEY (NCT03594110)]. This trial was designed to determine the treatment effect of empagliflozin compared to placebo in adults with CKD (with and without type 2 diabetes). The trial, which studied empagliflozin rather than SYNJARDY or SYNJARDY XR, included adults taking metformin HCl as a concomitant medication. The efficacy results of EMPA-KIDNEY are reported below.

EMPA-KIDNEY was a randomized, double-blind, placebo-controlled trial conducted in adults with chronic kidney disease [eGFR ≥20 to <45 mL/min/1.73 m^2; or eGFR ≥45 to <90 mL/min/1.73 m^2 with urine albumin to creatinine ratio (UACR) ≥200 mg/g]. The trial excluded patients with polycystic kidney disease or patients requiring intravenous immunosuppressive therapy in the preceding three months or >45 mg of prednisone (or equivalent) at the time of screening. The primary objective of the trial was to assess the effects of empagliflozin as an adjunct to standard of care therapy, including RAS-inhibitor therapy when appropriate, on time to kidney disease progression or CV death. A total of 6,609 patients, were equally randomized to empagliflozin 10 mg orally once-daily or placebo and were followed for a median of 24 months.

Baseline Disease Characteristics and Demographics

EMPA-KIDNEY included patients with type 2 diabetes mellitus (n=2,936) and patients without type 2 diabetes mellitus (n=3,673). The mean age of the study population was 63 years (range: 18 to 94 years) and 67% were male. Approximately 58% of the study population were White, 36% Asian, and 4% Black or African American. At baseline, the mean eGFR was 37 mL/min/1.73 m^2, 21% of patients had an eGFR equal to or above 45 mL/min/1.73 m^2, and 44% had an eGFR 30 to less than 45 mL/min/1.73 m^2. The median UACR was 329 mg/g, 20% of patients had a UACR <30 mg/g, 28% had a UACR 30 to ≤300 mg/g, and 52% had a UACR >300 mg/g. The most common etiologies of CKD were diabetic nephropathy/diabetic kidney disease (31%), glomerular disease (25%), hypertensive/renovascular disease (22%) and other/unknown (22%). At baseline, 85% of patients were treated with angiotensin-converting enzyme (ACE) inhibitor or angiotensin receptor blocker (ARB), 64% with statins, and 34% with antiplatelet agents.

In EMPA-KIDNEY, history of type 2 diabetes mellitus was present in 44% of the patients, and 23% of these patients were treated with metformin HCl (329 patients in the empagliflozin group and 334 in the placebo group). In the type 2 diabetes mellitus subpopulation, the mean age was 68 years, 67% were males, 59% White, 33% Asian and 6% Black or African American. In the type 2 diabetes mellitus subpopulation, at baseline, the mean eGFR was 36 mL/min/1.73 m^2, 17% of patients had an eGFR equal to or above 45 mL/min/1.73 m^2, and 45% had an eGFR 30 to less than 45 mL/min/1.73 m^2; the median UACR was 256 mg/g, 22% of patients had a UACR <30 mg/g, 31% had a UACR 30 to ≤300 mg/g, and 47% had a UACR >300 mg/g. The most common etiologies of CKD at baseline in this subpopulation were diabetic nephropathy/diabetic kidney disease (67%), glomerular disease (6%), hypertensive/renovascular disease (14%) and other/unknown (13%). In this subpopulation, at baseline, 85% of patients were treated with ACE inhibitor or ARB, 79% with statins, and 48% with antiplatelet agents.

Results

In EMPA-KIDNEY, empagliflozin 10 mg, compared with placebo, reduced the risk of the primary composite endpoint of sustained ≥40% eGFR decline, sustained eGFR <10 mL/min/1.73 m^2, progression to end-stage kidney disease, or CV or renal death. The treatment effect reflected a reduction in a sustained ≥40% eGFR decline, sustained eGFR <10 mL/min/1.73 m^2, progression to end-stage kidney disease, and CV death. There were few renal deaths during the trial. Empagliflozin also reduced the risk of first and recurrent hospitalization; information collected on the reason for hospitalization was insufficient to further characterize the benefit. Because of the metformin HCl component, SYNJARDY and SYNJARDY XR are not indicated for use in patients with CKD without type 2 diabetes mellitus [see Indications and Usage (1)].

The effect of empagliflozin in reducing the risk of the primary composite endpoint was consistent in patients with type 2 diabetes mellitus [HR 0.65 (95% CI 0.54, 0.78)], and in patients with type 2 diabetes mellitus and metformin HCl as background therapy [HR 0.72 (95% CI 0.48, 1.09)].

16 HOW SUPPLIED/STORAGE AND HANDLING

SYNJARDY tablets are available as follows:

Tablet Strength | Color/Shape | Tablet Markings | Package Size | NDC Number
5 mg Empagliflozin 500 mg Metformin HCl | orange yellow, oval, biconvex, film-coated tablet | Boehringer Ingelheim company symbol and "S5" debossed on one side; the other side is debossed with "500". | Bottles of 60 Bottles of 180 | 0597-0159-60 0597-0159-18
5 mg Empagliflozin 1,000 mg Metformin HCl | brownish yellow, oval, biconvex, film-coated tablet | Boehringer Ingelheim company symbol and "S5" debossed on one side; the other side is debossed with "1000". | Bottles of 60 Bottles of 180 | 0597-0175-60 0597-0175-18
12.5 mg Empagliflozin 500 mg Metformin HCl | pale brownish purple, oval, biconvex, film-coated tablet | Boehringer Ingelheim company symbol and "S12" debossed on one side; the other side is debossed with "500". | Bottles of 60 Bottles of 180 | 0597-0180-60 0597-0180-18
12.5 mg Empagliflozin 1,000 mg Metformin HCl | dark brownish purple, oval, biconvex, film-coated tablet | Boehringer Ingelheim company symbol and "S12" debossed on one side; the other side is debossed with "1000". | Bottles of 60 Bottles of 180 | 0597-0168-60 0597-0168-18

SYNJARDY XR extended-release tablets are available as follows:

Tablet Strength | Color/Shape | Tablet Markings | Package Size | NDC Number
5 mg Empagliflozin 1,000 mg Metformin HCl | olive green, oval, biconvex, film-coated tablet | Printed on one side in black ink with the Boehringer Ingelheim company symbol and "S5" on the top line and "1000 M" on the bottom line. | Bottles of 60 Bottles of 180 | 0597-0290-74 0597-0290-59
10 mg Empagliflozin 1,000 mg Metformin HCl | orange, oval, biconvex, film-coated tablet | Printed on one side in black ink with the Boehringer Ingelheim company symbol and "S10" on the top line and "1000 M" on the bottom line. | Bottles of 30 Bottles of 90 | 0597-0280-73 0597-0280-90
12.5 mg Empagliflozin 1,000 mg Metformin HCl | blue, oval, biconvex, film-coated tablet | Printed on one side in black ink with the Boehringer Ingelheim company symbol and "S12" on the top line and "1000 M" on the bottom line. | Bottles of 60 Bottles of 180 | 0597-0300-45 0597-0300-93
25 mg Empagliflozin 1,000 mg Metformin HCl | light green, oval, biconvex, film-coated tablet | Printed on one side in black ink with the Boehringer Ingelheim company symbol and "S25" on the top line and "1000 M" on the bottom line. | Bottles of 30 Bottles of 90 | 0597-0295-88 0597-0295-78

Storage

Store at 20°C to 25°C (68°F to 77°F); excursions permitted to 15°C to 30°C (59°F to 86°F) [see USP Controlled Room Temperature].

17 PATIENT COUNSELING INFORMATION

Advise the patient to read the FDA-approved patient labeling (Medication Guide).

Lactic Acidosis

Inform patients of the risks of lactic acidosis due to metformin, its symptoms, and conditions that predispose to its development. Advise patients to discontinue SYNJARDY or SYNJARDY XR immediately and to notify their healthcare provider promptly if unexplained hyperventilation, malaise, myalgia, unusual somnolence, or other nonspecific symptoms occur. Counsel patients against excessive alcohol intake and inform patients about the importance of regular testing of renal function while receiving SYNJARDY or SYNJARDY XR. Instruct patients to inform their healthcare provider that they are taking SYNJARDY or SYNJARDY XR prior to any surgical or radiological procedure, as temporary discontinuation may be required until renal function has been confirmed to be normal [see Warnings and Precautions (5.1)].

Diabetic Ketoacidosis in Patients with Type 1 Diabetes Mellitus and Other Ketoacidosis

Inform patients that SYNJARDY or SYNJARDY XR can cause potentially fatal ketoacidosis and that type 2 diabetes mellitus and pancreatic disorders (e.g., history of pancreatitis or pancreatic surgery) are risk factors.

Educate all patients on precipitating factors (such as insulin dose reduction or missed insulin doses, infection, reduced caloric intake, ketogenic diet, surgery, dehydration, and alcohol abuse) and symptoms of ketoacidosis (including nausea, vomiting, abdominal pain, tiredness, and labored breathing). Inform patients that blood glucose may be normal even in the presence of ketoacidosis.

Advise patients that they may be asked to monitor ketones. If symptoms of ketoacidosis occur, instruct patients to discontinue SYNJARDY or SYNJARDY XR and seek medical attention immediately [see Warnings and Precautions (5.2)].

Volume Depletion

Inform patients that symptomatic hypotension may occur with SYNJARDY or SYNJARDY XR and advise them to contact their healthcare provider if they experience such symptoms [see Warnings and Precautions (5.3)]. Inform patients that dehydration may increase the risk for hypotension, and to maintain adequate fluid intake.

Genitourinary Infections, including Urosepsis, Pyelonephritis, Necrotizing Fasciitis of the Perineum (Fournier's Gangrene), and Genital Mycotic Infections

Counsel patients that genitourinary infections may occur when taking empagliflozin, a component of SYNJARDY and SYNJARDY XR, and may become serious. Educate them on the symptoms and advise them to seek medical advice if symptoms occur. Specifically, advise patients to promptly seek medical attention if they develop pain or tenderness, redness, or swelling of the genitals or the area from the genitals back to the rectum, along with a fever above 100.4°F or malaise [see Warnings and Precautions (5.4)].

Hypoglycemia

Inform patients that hypoglycemia has been reported when SYNJARDY or SYNJARDY XR is used with insulin secretagogues or insulin. Hypoglycemia may occur in pediatric patients regardless of concomitant antidiabetic treatment. Educate patients or caregivers on the signs and symptoms of hypoglycemia [see Warnings and Precautions (5.5)].

Lower Limb Amputation

Counsel patients about the importance of routine preventative foot care. Instruct patients to monitor for new pain or tenderness, sores or ulcers, or infections involving the leg or foot and to seek medical advice immediately if such signs or symptoms develop [see Warnings and Precautions (5.6)].

Hypersensitivity Reactions

Inform patients that serious hypersensitivity reactions, such as urticaria and angioedema, have been reported with empagliflozin, a component of SYNJARDY and SYNJARDY XR. Advise patients to report immediately any skin reaction or angioedema, and to discontinue the drug until they have consulted prescribing healthcare provider [see Warnings and Precautions (5.7)].

Vitamin B12 Deficiency

Inform patients about the importance of regular hematological parameters while receiving SYNJARDY or SYNJARDY XR [see Warnings and Precautions (5.8)].

Laboratory Tests

Inform patients that elevated glucose in urinalysis is expected when taking SYNJARDY or SYNJARDY XR [see Drug Interactions (7)].

Pregnancy

Advise pregnant patients, and patients of reproductive potential, of the potential risk to a fetus with treatment with SYNJARDY or SYNJARDY XR [see Use in Specific Populations (8.1)]. Instruct patients to report pregnancies to their healthcare provider as soon as possible.

Lactation

Advise patients that breastfeeding is not recommended during treatment with SYNJARDY or SYNJARDY XR [see Use in Specific Populations (8.2)].

Patients of Reproductive Potential

Inform patients that treatment with metformin HCl may result in ovulation in some premenopausal anovulatory patients, which may lead to unintended pregnancy [see Use in Specific Populations (8.3)].

Administration Instructions

Inform patients that SYNJARDY XR tablets must be swallowed whole and never split, crushed, dissolved, or chewed and that incompletely dissolved SYNJARDY XR tablets may be eliminated in the feces.

Missed Dose

Instruct patients to take SYNJARDY or SYNJARDY XR only as prescribed. If a dose is missed, it should be taken as soon as the patient remembers. Advise patients not to double their next dose [see Dosage and Administration (2.7)].

Distributed by:
Boehringer Ingelheim Pharmaceuticals, Inc.
Ridgefield, CT 06877 USA

Licensed from:
Boehringer Ingelheim International GmbH, Ingelheim, Germany

SYNJARDY is a registered trademark of and used under license from Boehringer Ingelheim International GmbH.

Boehringer Ingelheim Pharmaceuticals, Inc. either owns or uses the Jardiance®, EMPA-REG OUTCOME®, EMPEROR-Reduced®, EMPEROR-Preserved®, and EMPA-KIDNEY® trademarks under license.

The other brands listed are trademarks of their respective owners and are not trademarks of Boehringer Ingelheim Pharmaceuticals, Inc.

Copyright © 2026 Boehringer Ingelheim International GmbH
ALL RIGHTS RESERVED

COL12574FA072026

SPL8975O

MEDICATION GUIDE
SYNJARDY® (sin-JAR-dee)
(empagliflozin and metformin hydrochloride tablets), for oral use
and
SYNJARDY® XR (sin-JAR-dee XR)
(empagliflozin and metformin hydrochloride extended-release tablets), for oral use

What is the most important information I should know about SYNJARDY or SYNJARDY XR?
SYNJARDY or SYNJARDY XR can cause serious side effects, including:

- Lactic Acidosis. Metformin hydrochloride (HCl), one of the medicines in SYNJARDY and SYNJARDY XR, can cause a rare but serious condition called lactic acidosis (a build-up of lactic acid in the blood) that can cause death. Lactic acidosis is a medical emergency and must be treated in a hospital.
  Stop taking SYNJARDY or SYNJARDY XR and call your healthcare provider right away or go to the nearest hospital emergency room if you get any of the following symptoms of lactic acidosis:

- feel very weak and tired
- have unusual (not normal) muscle pain
- have trouble breathing
- have unexplained stomach or intestinal problems with nausea and vomiting, or diarrhea

- have unusual sleepiness or sleep longer than usual
- feel cold, especially in your arms and legs
- feel dizzy or lightheaded
- have a slow or irregular heartbeat

You have a higher chance of getting lactic acidosis with SYNJARDY or SYNJARDY XR if you:

- have moderate to severe kidney problems.
- have liver problems.
- drink a lot of alcohol (very often or short-term "binge" drinking).
- get dehydrated (lose a large amount of body fluids). This can happen if you are sick with a fever, vomiting, or diarrhea. Dehydration can also happen when you sweat a lot with activity or exercise and do not drink enough fluids.
- have certain x-ray tests with injectable dyes or contrast agents.
- have surgery or other procedure for which you need to restrict the amount of food and liquid you eat and drink.
- have congestive heart failure.
- have a heart attack, severe infection, or stroke.
- are 65 years of age or older.

Tell your healthcare provider if you have any of the problems in the list above. Tell your healthcare provider that you are taking SYNJARDY or SYNJARDY XR before you have surgery or x-ray tests. Your healthcare provider may need to stop your SYNJARDY or SYNJARDY XR for a while if you have surgery or certain x-ray tests. SYNJARDY or SYNJARDY XR can have other serious side effects. See "What are the possible side effects of SYNJARDY or SYNJARDY XR?"

- Diabetic ketoacidosis (increased ketones in your blood or urine) in people with type 1 and other ketoacidosis. SYNJARDY or SYNJARDY XR can cause ketoacidosis that can be life-threatening and may lead to death. Ketoacidosis is a serious condition which needs to be treated in a hospital. People with type 1 diabetes have a high risk of getting ketoacidosis. People with type 2 diabetes or pancreas problems also have an increased risk of getting ketoacidosis. Ketoacidosis can also happen in people who: are sick, cannot eat or drink as usual, skip meals, are on a diet high in fat and low in carbohydrates (ketogenic diet), take less than the usual amount of insulin or miss insulin doses, drink too much alcohol, have a loss of too much fluid from the body (volume depletion), or who have surgery. Ketoacidosis can happen even if your blood sugar is less than 250 mg/dL. Your healthcare provider may ask you to periodically check ketones in your urine or blood.
  Stop taking SYNJARDY or SYNJARDY XR and call your healthcare provider or get medical help right away if you get any of the following. If possible, check for ketones in your urine or blood, even if your blood sugar is less than 250 mg/dL:

- nausea
- vomiting
- stomach-area (abdominal) pain

- tiredness
- trouble breathing
- ketones in your urine or blood

- Dehydration. SYNJARDY or SYNJARDY XR can cause some people to become dehydrated (the loss of body water and salt). Dehydration may cause you to feel dizzy, faint, light-headed, or weak, especially when you stand up (orthostatic hypotension). There have been reports of sudden worsening of kidney function in people who are taking SYNJARDY or SYNJARDY XR. You may be at higher risk of dehydration if you:
  - take medicines to lower your blood pressure, including diuretics (water pills)
  - are on a low sodium (salt) diet
  - have kidney problems
  - are 65 years of age or older
  Talk to your healthcare provider about what you can do to prevent dehydration including how much fluid you should drink on a daily basis. Call your healthcare provider right away if you reduce the amount of food or liquid you drink, for example if you are sick or you cannot eat, or start to lose liquids from your body, for example from vomiting, diarrhea or being in the sun too long.

What is SYNJARDY or SYNJARDY XR?

- SYNJARDY is a prescription medicine that contains 2 diabetes medicines, empagliflozin (JARDIANCE) and metformin HCl immediate-release.
- SYNJARDY XR is a prescription medicine that contains 2 diabetes medicines, empagliflozin (JARDIANCE) and metformin HCl extended-release.
- SYNJARDY can be used along with diet and exercise to improve blood sugar (glucose) in adults and children who are 10 years of age and older with type 2 diabetes.
- SYNJARDY XR can be used along with diet and exercise to improve blood sugar (glucose) in adults with type 2 diabetes.
- One of the medicines in SYNJARDY and SYNJARDY XR, empagliflozin (JARDIANCE), can also be used in adults with type 2 diabetes:
  - who have known cardiovascular disease to reduce the risk of cardiovascular death.
  - who have heart failure (when the heart cannot pump enough blood to the rest of your body) to reduce the risk of cardiovascular death and hospitalization for heart failure.
  - to reduce the risk of further worsening of kidney disease, end-stage kidney disease (ESKD), death due to cardiovascular disease, and hospitalization in adults with chronic kidney disease.
- SYNJARDY or SYNJARDY XR is not for use to lower blood sugar (glucose) in people with type 1 diabetes. It may increase their risk of diabetic ketoacidosis (increased ketones in blood or urine).
- SYNJARDY or SYNJARDY XR is only for use in people with type 2 diabetes, because it contains the prescription medicine metformin HCl.
- One of the medicines in SYNJARDY or SYNJARDY XR, empagliflozin (JARDIANCE), is not for people with polycystic kidney disease, or who are taking or have recently received certain types of immunosuppressive therapy to treat kidney disease. Empagliflozin (JARDIANCE) is not expected to work if you have these conditions.
- It is not known if SYNJARDY is safe and effective in children under 10 years of age.
- It is not known if SYNJARDY XR is safe and effective in children.

Who should not take SYNJARDY or SYNJARDY XR?
Do not take SYNJARDY or SYNJARDY XR if you:

- have severe kidney problems.
- have a condition called metabolic acidosis or diabetic ketoacidosis (increased ketones in the blood or urine).
- are allergic to empagliflozin (JARDIANCE), metformin HCl, or any of the ingredients in SYNJARDY or SYNJARDY XR.
  See the end of this Medication Guide for a complete list of ingredients in SYNJARDY and SYNJARDY XR. Symptoms of a serious allergic reaction to SYNJARDY and SYNJARDY XR may include:
  - rash
  - raised, red areas on your skin (hives)
  - swelling of your face, lips, mouth, and throat that may cause difficulty in breathing or swallowing
  If you have any of these symptoms, stop taking SYNJARDY or SYNJARDY XR and call your healthcare provider right away or go to the nearest hospital emergency room.

What should I tell my healthcare provider before taking SYNJARDY or SYNJARDY XR?
Before taking SYNJARDY or SYNJARDY XR, tell your healthcare provider about all of your medical conditions, including if you:

- have type 1 diabetes or have had diabetic ketoacidosis.
- have a decrease in your insulin dose.
- have a serious infection.
- have a history of infection of the vagina or penis.
- have a history of amputation.
- have kidney problems.
- have liver problems.
- have heart problems, including congestive heart failure.
- are 65 years of age or older.
- have a history of urinary tract infections or problems with urination.
- are on a low sodium (salt) diet. Your healthcare provider may change your diet or your dose.
- are going to have surgery. Your healthcare provider may stop your SYNJARDY or SYNJARDY XR before you have surgery. Talk to your healthcare provider if you are having surgery about when to stop taking SYNJARDY or SYNJARDY XR and when to start it again.
- are eating less, or there is a change in your diet.
- are dehydrated.
- have or have had problems with your pancreas, including pancreatitis or surgery on your pancreas.
- drink alcohol very often or drink a lot of alcohol in the short term ("binge" drinking).
- have ever had an allergic reaction to SYNJARDY or SYNJARDY XR.
- are going to get an injection of dye or contrast agents for an x-ray procedure. SYNJARDY or SYNJARDY XR may need to be stopped for a short time. Talk to your healthcare provider about when you should stop SYNJARDY or SYNJARDY XR and when you should start SYNJARDY or SYNJARDY XR again. See "What is the most important information I should know about SYNJARDY or SYNJARDY XR?"
- have low levels of vitamin B12 in your blood.
- are pregnant or plan to become pregnant. SYNJARDY or SYNJARDY XR may harm your unborn baby. If you become pregnant while taking SYNJARDY or SYNJARDY XR, tell your healthcare provider as soon as possible. Talk with your healthcare provider about the best way to control your blood sugar while you are pregnant.
- are breastfeeding or plan to breastfeed. SYNJARDY or SYNJARDY XR may pass into your breast milk and may harm your baby. Talk with your healthcare provider about the best way to feed your baby if you are taking SYNJARDY or SYNJARDY XR. Do not breastfeed while taking SYNJARDY or SYNJARDY XR.
- are a person who has not gone through menopause (premenopausal) who does not have periods regularly or at all. SYNJARDY or SYNJARDY XR can cause the release of an egg from an ovary in a person (ovulation). This can increase your chance of getting pregnant. Tell your healthcare provider right away if you become pregnant while taking SYNJARDY or SYNJARDY XR.

Tell your healthcare provider about all the medicines you take, including prescription and over-the-counter medicines, vitamins, and herbal supplements.
SYNJARDY or SYNJARDY XR may affect the way other medicines work, and other medicines may affect how SYNJARDY or SYNJARDY XR works. Know the medicines you take. Keep a list of them to show your healthcare provider and pharmacist when you get a new medicine.

How should I take SYNJARDY or SYNJARDY XR?

- Take SYNJARDY or SYNJARDY XR exactly as your healthcare provider tells you to take it.
- If you are prescribed SYNJARDY:
  - take SYNJARDY by mouth 2 times each day with meals. Taking SYNJARDY with meals may lower your chance of having an upset stomach.
- If you are prescribed SYNJARDY XR:
  - take SYNJARDY XR by mouth 1 time each day with a meal in the morning. Taking SYNJARDY XR with a meal may lower your chance of having an upset stomach.
  - swallow SYNJARDY XR tablets whole. Do not break, cut, crush, dissolve, or chew SYNJARDY XR tablets. If you cannot swallow SYNJARDY XR tablets whole, tell your healthcare provider.
  - you may see something that looks like the SYNJARDY XR tablet in your stool (bowel movement). This is not harmful and should not affect the way SYNJARDY XR works to control your diabetes.
- Your healthcare provider will tell you how much SYNJARDY or SYNJARDY XR to take and when to take it. Your healthcare provider may change your dose if needed.
- Your healthcare provider may tell you to take SYNJARDY or SYNJARDY XR along with other diabetes medicines. Low blood sugar can happen more often when SYNJARDY or SYNJARDY XR is taken with certain other diabetes medicines. See "What are the possible side effects of SYNJARDY or SYNJARDY XR?"
- If you miss a dose, take it as soon as you remember. If it is almost time for your next dose, skip the missed dose and take the medicine at the next regularly scheduled time. Do not take two doses of SYNJARDY or SYNJARDY XR at the same time. Talk with your healthcare provider if you have questions about a missed dose.
- If you take too much SYNJARDY or SYNJARDY XR, call your healthcare provider or Poison Help line at 1-800-222-1222, or go to the nearest hospital emergency room right away.
- When taking SYNJARDY or SYNJARDY XR, you may have sugar in your urine, which will show up on a urine test.
- When your body is under some types of stress, such as fever, trauma (such as a car accident), infection, or surgery, the amount of diabetes medicine you need may change. Tell your healthcare provider right away if you have any of these conditions and follow your healthcare provider's instructions.
- Your healthcare provider may do certain blood tests before you start SYNJARDY or SYNJARDY XR and during your treatment as needed.

What should I avoid while taking SYNJARDY or SYNJARDY XR?
Avoid drinking alcohol very often, or drinking a lot of alcohol in a short period of time ("binge" drinking). It can increase your chances of getting serious side effects.

What are the possible side effects of SYNJARDY or SYNJARDY XR?
SYNJARDY or SYNJARDY XR may cause serious side effects, including:

- See "What is the most important information I should know about SYNJARDY or SYNJARDY XR?"
- Genital and urinary tract infections. Empagliflozin, one of the medicines in SYNJARDY and SYNJARDY XR, can cause serious infections in your genital area or urinary tract that could require hospitalization. A rare but serious bacterial infection called necrotizing fasciitis can cause damage to the tissue under the skin in the area between and around the anus and genitals (perineum). This infection may require hospitalization, multiple surgeries, and could lead to death. Seek medical attention immediately if you have a fever or you are feeling very weak, tired or uncomfortable (malaise), and you develop any of the following symptoms in the area between and around your anus and genitals:

- pain or tenderness

- swelling

- redness of skin (erythema)

Also tell your healthcare provider if you have any of these signs or symptoms of urinary tract infections or yeast infections:

- Urinary tract infection:
  - burning feeling when you urinate
  - need to urinate often or right away
  - pain in the lower part of your stomach (pelvis)
  - blood in your urine

You may also have a fever, back pain, nausea, or vomiting.

- Vaginal yeast infection:
  - vaginal odor
  - white or yellowish vaginal discharge (may be lumpy or look like cottage cheese)
  - vaginal itching

- Yeast infection of the skin around the penis (balanitis or balanoposthitis): If you are uncircumcised, swelling may make it difficult to pull back the skin around the tip of your penis. Other symptoms include:

- redness, itching, or swelling of the penis
- bad smelling discharge from the penis

- rash on the penis
- pain in the skin around the penis

Talk to your healthcare provider about what to do if you get symptoms of a yeast infection. They may suggest you use an over-the-counter antifungal medicine. Contact your healthcare provider right away if your symptoms do not improve after using an over-the-counter antifungal medicine.

- Low blood sugar (hypoglycemia). In adults, if you take SYNJARDY or SYNJARDY XR with another medicine that can cause low blood sugar, such as a sulfonylurea or insulin, your risk of getting low blood sugar is higher. In children 10 years of age and older, the risk for low blood sugar is higher with SYNJARDY even if you do not use another medicine that can also lower blood sugar. The dose of your sulfonylurea medicine or insulin may need to be lowered while you take SYNJARDY or SYNJARDY XR.
  Signs and symptoms of low blood sugar may include:

- headache
- drowsiness
- weakness

- irritability
- hunger
- fast heartbeat

- confusion
- shaking or feeling jittery

- dizziness
- sweating

- Amputations. SGLT2 inhibitors may increase your risk of lower limb amputations.
  You may be at a higher risk of lower limb amputation if you:
  - have a history of amputation
  - have had blocked or narrowed blood vessels, usually in your leg
  - have had diabetic foot infection, ulcers or sores
  Call your healthcare provider right away if you have new pain or tenderness, any sores, ulcers, or infections in your leg or foot. Talk to your healthcare provider about proper foot care.
- Serious allergic reactions. If you have any symptoms of a serious allergic reaction, stop taking SYNJARDY or SYNJARDY XR and call your healthcare provider right away or go to the nearest hospital emergency room. See "Who should not take SYNJARDY or SYNJARDY XR?".
- Low vitamin B12 (vitamin B12 deficiency). Using metformin for long periods of time may cause a decrease in the amount of vitamin B12 in your blood, especially if you have had low vitamin B12 blood levels before. Your healthcare provider may do blood tests to check your vitamin B12 levels.

The most common side effects of SYNJARDY or SYNJARDY XR include:

- low blood sugar
- urinary tract infections
- stuffy or runny nose and sore throat
- yeast infections in females
- diarrhea
- nausea or vomiting

- gas
- stomach discomfort
- indigestion
- weakness
- headache

These are not all the possible side effects of SYNJARDY or SYNJARDY XR. For more information, ask your healthcare provider or pharmacist.
Call your doctor for medical advice about side effects. You may report side effects to FDA at 1-800-FDA-1088.

How should I store SYNJARDY or SYNJARDY XR?

- Store SYNJARDY or SYNJARDY XR at room temperature between 68°F to 77°F (20°C to 25°C).
- Keep SYNJARDY or SYNJARDY XR and all medicines out of the reach of children.

General information about the safe and effective use of SYNJARDY or SYNJARDY XR.
Medicines are sometimes prescribed for purposes other than those listed in a Medication Guide. Do not use SYNJARDY or SYNJARDY XR for a condition for which it was not prescribed. Do not give SYNJARDY or SYNJARDY XR to other people, even if they have the same symptoms that you have. It may harm them.
You can ask your pharmacist or healthcare provider for information about SYNJARDY or SYNJARDY XR that is written for health professionals.

What are the ingredients in SYNJARDY?
Active Ingredients: empagliflozin and metformin HCl
Inactive Ingredients: colloidal silicon dioxide, copovidone, corn starch, and magnesium stearate. In addition, the film coating contains the following inactive ingredients: hypromellose, polyethylene glycol 400, talc, and titanium dioxide. 5 mg/500 mg and 5 mg/1,000 mg tablets also contain ferric oxide yellow. 12.5 mg/500 mg and 12.5 mg/1,000 mg tablets also contain black ferrosoferric oxide and ferric oxide red.
What are the ingredients in SYNJARDY XR?
Active Ingredients: empagliflozin and metformin HCl
Inactive Ingredients: Tablet core contains: hypromellose, magnesium stearate, and polyethylene oxide. The film coatings and printing ink contain: carnauba wax, FD&C blue#2/indigo carmine aluminum lake (12.5 mg/1,000 mg, 25 mg/1,000 mg), ferric oxide red (10 mg/1,000 mg), ferric oxide yellow (5 mg/1,000 mg, 10 mg/1,000 mg, 25 mg/1,000 mg), ferrosoferric oxide, hypromellose, isopropyl alcohol, polydextrose, polyethylene glycol, propylene glycol, purified water, talc, and titanium dioxide.

Distributed by: Boehringer Ingelheim Pharmaceuticals, Inc., Ridgefield, CT 06877 USA
Licensed from: Boehringer Ingelheim International GmbH, Ingelheim, Germany
SYNJARDY is a registered trademark of and used under license from Boehringer Ingelheim International GmbH.
Boehringer Ingelheim Pharmaceuticals, Inc. either owns or uses the Jardiance®, EMPA-REG OUTCOME®, EMPEROR-Reduced®, EMPEROR-Preserved®, and EMPA-KIDNEY® trademarks under license.
The other brands listed are trademarks of their respective owners and are not trademarks of Boehringer Ingelheim Pharmaceuticals, Inc.
Copyright © 2026 Boehringer Ingelheim International GmbH
ALL RIGHTS RESERVED
COL12574FA072026
For more information about SYNJARDY or SYNJARDY XR, including current prescribing information and Medication Guide, go to www.synjardy.com or www.synjardyxr.com, scan the code, or call Boehringer Ingelheim Pharmaceuticals, Inc. at 1-800-542-6257.

This Medication Guide has been approved by the U.S. Food and Drug Administration.

Revised: January 2026

PRINCIPAL DISPLAY PANEL - 5 mg/500 mg Tablet Bottle Label

NDC 0597-0159-60

DISPENSE WITH ACCOMPANYING
MEDICATION GUIDE

Synjardy®
(empagliflozin and
metformin
hydrochloride tablets)

5 mg/500 mg*

Rx only

60 tablets

Boehringer
Ingelheim

PRINCIPAL DISPLAY PANEL - 5 mg/1,000 mg Tablet Bottle Label

NDC 0597-0175-60

DISPENSE WITH ACCOMPANYING
MEDICATION GUIDE

Synjardy®
(empagliflozin and
metformin
hydrochloride tablets)

5 mg/1,000 mg*

Rx only

60 tablets

Boehringer
Ingelheim

PRINCIPAL DISPLAY PANEL - 12.5 mg/500 mg Tablet Bottle Label

NDC 0597-0180-60

DISPENSE WITH ACCOMPANYING
MEDICATION GUIDE

Synjardy®
(empagliflozin and
metformin
hydrochloride tablets)

12.5 mg/500 mg*

Rx only

60 tablets

Boehringer
Ingelheim

PRINCIPAL DISPLAY PANEL - 12.5 mg/1,000 mg Tablet Bottle Label

NDC 0597-0168-60

DISPENSE WITH ACCOMPANYING
MEDICATION GUIDE

Synjardy®
(empagliflozin and
metformin
hydrochloride tablets)

12.5 mg/1,000 mg*

Rx only

60 tablets

Boehringer
Ingelheim